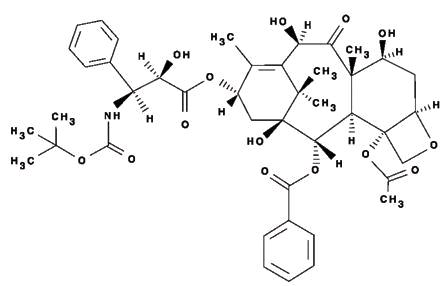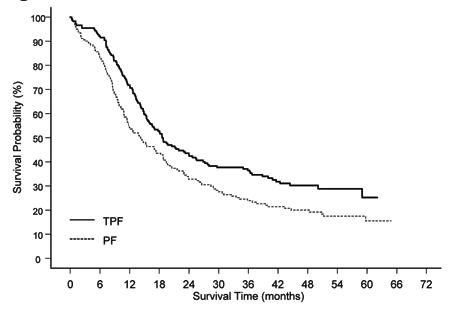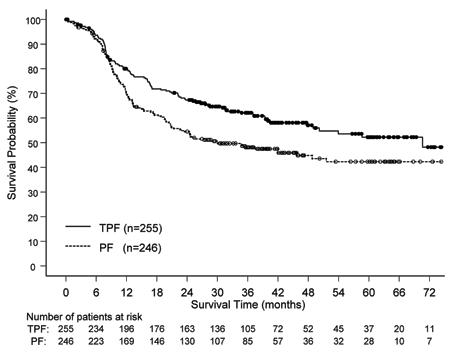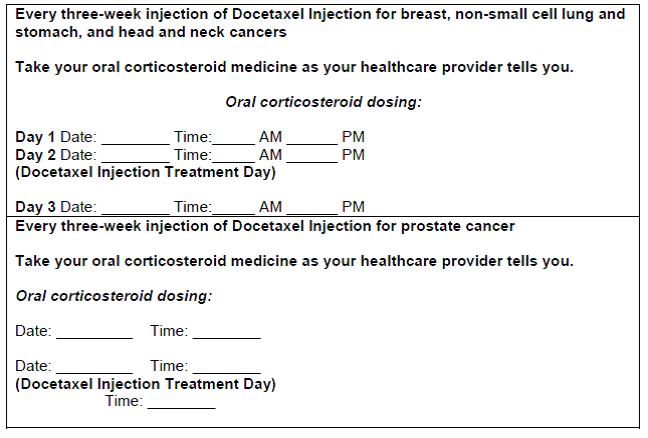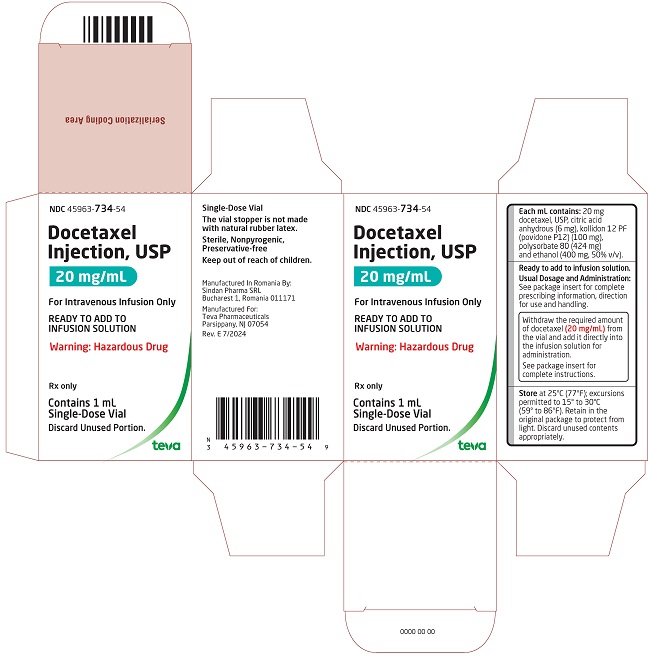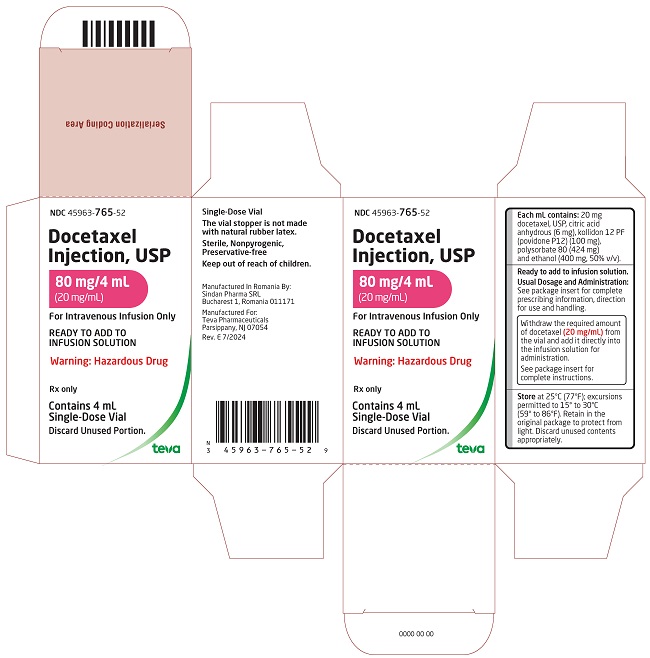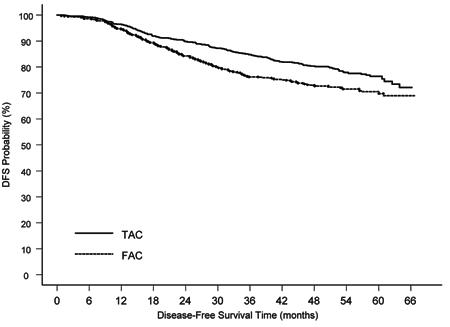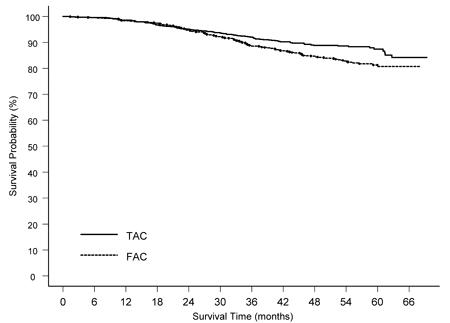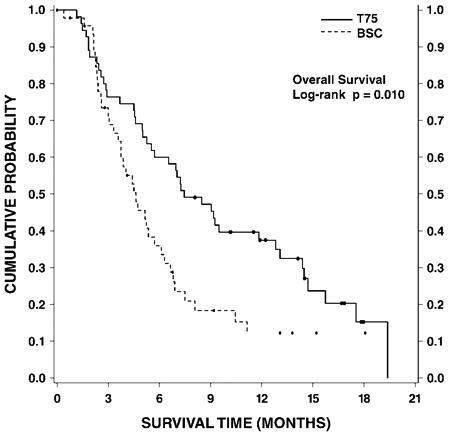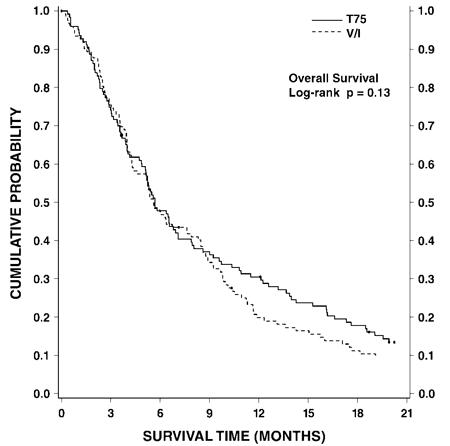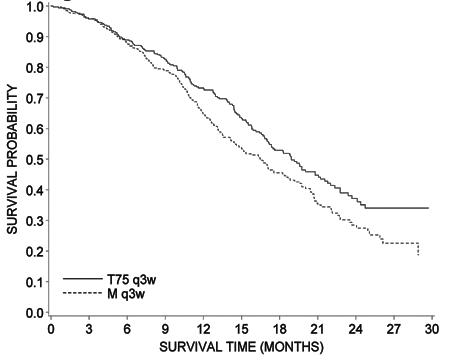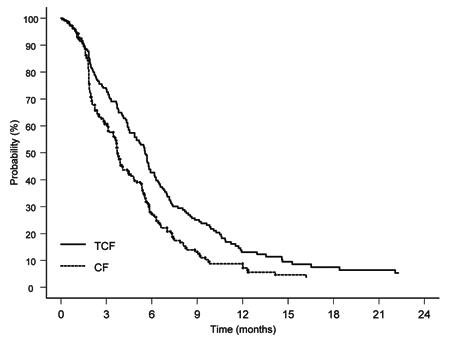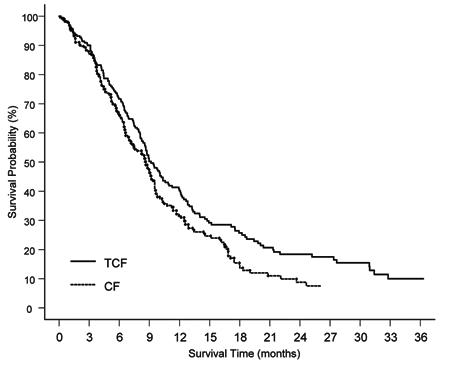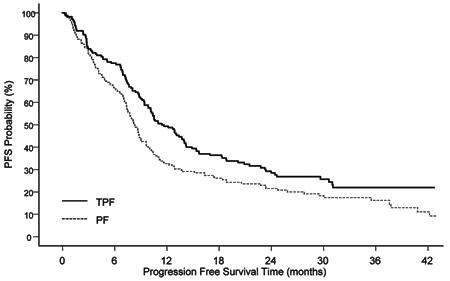 DRUG LABEL: Docetaxel
NDC: 45963-734 | Form: INJECTION, SOLUTION, CONCENTRATE
Manufacturer: Actavis Pharma, Inc.
Category: prescription | Type: HUMAN PRESCRIPTION DRUG LABEL
Date: 20240801

ACTIVE INGREDIENTS: DOCETAXEL 20 mg/1 mL
INACTIVE INGREDIENTS: ANHYDROUS CITRIC ACID; POVIDONE K12; POLYSORBATE 80; ALCOHOL

HIGHLIGHTS OF PRESCRIBING INFORMATION

These highlights do not include all the information needed to use DOCETAXEL INJECTION safely and effectively. See full prescribing information for DOCETAXEL INJECTION.
DOCETAXEL injection, for intravenous use
Initial U.S. Approval: 1996

WARNING: TOXIC DEATHS, HEPATOTOXICITY, NEUTROPENIA, HYPERSENSITIVITY REACTIONS, and FLUID RETENTION

See full prescribing information for complete boxed warning.

- Treatment-related mortality increases with abnormal liver function, at higher doses, and in patients with NSCLC and prior platinum-based therapy receiving Docetaxel Injection at 100 mg/m^2 (5.1)
- Avoid use of Docetaxel Injection if bilirubin > ULN, or if AST and/or ALT >1.5 x ULN concomitant with alkaline phosphatase >2.5 x ULN. LFT elevations increase risk of severe or life-threatening complications. Obtain LFTs before each treatment cycle (5.2)
- Do not administer Docetaxel Injection to patients with neutrophil counts <1500 cells/mm^3. Obtain frequent blood counts to monitor for neutropenia (4, 5.3)
- Severe hypersensitivity, including fatal anaphylaxis, has been reported in patients who received dexamethasone premedication. Severe reactions require immediate discontinuation of Docetaxel Injection and administration of appropriate therapy (5.5)
- Contraindicated if history of severe hypersensitivity reactions to Docetaxel Injection or to drugs formulated with polysorbate 80 (4)
- Severe fluid retention may occur despite dexamethasone (5.6)

1 INDICATIONS AND USAGE

Docetaxel Injection is a microtubule inhibitor indicated for:

- Breast Cancer (BC): single agent for locally advanced or metastatic BC after chemotherapy failure; and with doxorubicin and cyclophosphamide as adjuvant treatment of operable node-positive BC (1.1)
- Non-Small Cell Lung Cancer (NSCLC): single agent for locally advanced or metastatic NSCLC after platinum therapy failure; and with cisplatin for unresectable, locally advanced or metastatic untreated NSCLC (1.2)
- Castration-Resistant Prostate Cancer (CRPC): with prednisone in metastatic castration-resistant prostate cancer (1.3)
- Gastric Adenocarcinoma (GC): with cisplatin and fluorouracil for untreated, advanced GC, including the gastroesophageal junction (1.4)
- Squamous Cell Carcinoma of the Head and Neck (SCCHN): with cisplatin and fluorouracil for induction treatment of locally advanced SCCHN (1.5)

2 DOSAGE AND ADMINISTRATION

Administer in a facility equipped to manage possible complications (e.g., anaphylaxis). Administer intravenously (IV) over 1 hr every 3 weeks. PVC equipment is not recommended. Use only a 21 gauge needle to withdraw Docetaxel Injection from the vial.

- BC locally advanced or metastatic: 60 mg/m^2 to 100 mg/m^2 single agent (2.1)
- BC adjuvant: 75 mg/m^2 administered 1 hour after doxorubicin 50 mg/m^2 and cyclophosphamide 500 mg/m^2 every 3 weeks for 6 cycles (2.1)
- NSCLC: after platinum therapy failure: 75 mg/m^2 single agent (2.2)
- NSCLC: chemotherapy-naive: 75 mg/m^2 followed by cisplatin 75 mg/m^2 (2.2)
- CRPC: 75 mg/m^2 with 5 mg prednisone twice a day continuously (2.3)
- GC: 75 mg/m^2 followed by cisplatin 75 mg/m^2 (both on day 1 only) followed by fluorouracil 750 mg/m^2 per day as a 24-hr IV (days 1 to 5), starting at end of cisplatin infusion (2.4)
- SCCHN: 75 mg/m^2 followed by cisplatin 75 mg/m^2 IV (day 1), followed by fluorouracil 750 mg/m^2 per day as a 24-hr IV (days 1 to 5), starting at end of cisplatin infusion; for 4 cycles (2.5)
- SCCHN: 75 mg/m^2 followed by cisplatin 100 mg/m^2 IV (day 1), followed by fluorouracil 1000 mg/m^2 per day as a 24-hr IV (days 1 to 4); for 3 cycles (2.5)

For all patients:

- Premedicate with oral corticosteroids (2.6)
- Adjust dose as needed (2.7)

3 DOSAGE FORMS AND STRENGTHS

- Injection: One-vial Docetaxel: Single-Dose vials 20 mg/mL and 80 mg/4 mL (3)

4 CONTRAINDICATIONS

- Hypersensitivity to docetaxel or polysorbate 80 (4)
- Neutrophil counts of <1500 cells/mm^3 (4)

5 WARNINGS AND PRECAUTIONS

- Second primary malignancies: In patients treated with Docetaxel Injection-containing regimens, monitor for delayed AML, MDS, NHL, and renal cancer. (5.7)
- Cutaneous reactions: Reactions including erythema of the extremities with edema followed by desquamation may occur. Severe cutaneous adverse reactions have been reported. Severe skin toxicity may require dose adjustment or permanent treatment discontinuation. (5.8)
- Neurologic reactions: Reactions including paresthesia, dysesthesia, and pain may occur. Severe neurosensory symptoms require dose adjustment or discontinuation if persistent. (5.9)
- Eye disorders: Cystoid macular edema (CME) has been reported and requires treatment discontinuation. (5.10)
- Asthenia: Severe asthenia may occur and may require treatment discontinuation. (5.11)
- Embryo-fetal toxicity: Can cause fetal harm. Advise patients of the potential risk to a fetus and to use effective contraception. (5.12, 8.1, 8.3)
- Alcohol content: The alcohol content in a dose of Docetaxel Injection may affect the central nervous system. This may include impairment of a patient’s ability to drive or use machines immediately after infusion. (5.13)
- Tumor lysis syndrome: Tumor lysis syndrome has been reported. Patients at risk should be well hydrated and closely monitored during treatment. (5.14)

6 ADVERSE REACTIONS

Most common adverse reactions across all Docetaxel Injection indications are infections, neutropenia, anemia, febrile neutropenia, hypersensitivity, thrombocytopenia, neuropathy, dysgeusia, dyspnea, constipation, anorexia, nail disorders, fluid retention, asthenia, pain, nausea, diarrhea, vomiting, mucositis, alopecia, skin reactions, and myalgia. (6)

To report SUSPECTED ADVERSE REACTIONS, contact Teva at 1-888-838-2872 or FDA at 1-800-FDA-1088 or www.fda.gov/medwatch.

7 DRUG INTERACTIONS

- Cytochrome P450 3A4 inducers, inhibitors, or substrates: May alter docetaxel metabolism. (7)

8 USE IN SPECIFIC POPULATIONS

- Lactation: Advise women not to breastfeed. (8.2)
- Females and Males of Reproductive Potential: Verify pregnancy status of females prior to initiation of Docetaxel Injection. (8.3)

FULL PRESCRIBING INFORMATION

WARNING: TOXIC DEATHS, HEPATOTOXICITY, NEUTROPENIA, HYPERSENSITIVITY REACTIONS, and FLUID RETENTION

Treatment-related mortality associated with Docetaxel Injection is increased in patients with abnormal liver function, in patients receiving higher doses, and in patients with non-small cell lung carcinoma and a history of prior treatment with platinum-based chemotherapy who receive Docetaxel Injection as a single agent at a dose of 100 mg/m^2 [see Warnings and Precautions (5.1)].

Avoid the use of Docetaxel Injection in patients with bilirubin > upper limit of normal (ULN), or to patients with AST and/or ALT >1.5 x ULN concomitant with alkaline phosphatase >2.5 x ULN. Patients with elevations of bilirubin or abnormalities of transaminase concurrent with alkaline phosphatase are at increased risk for the development of severe neutropenia, febrile neutropenia, infections, severe thrombocytopenia, severe stomatitis, severe skin toxicity, and toxic death. Patients with isolated elevations of transaminase >1.5 x ULN also had a higher rate of febrile neutropenia. Measure bilirubin, AST or ALT, and alkaline phosphatase prior to each cycle of Docetaxel Injection [see Warnings and Precautions (5.2)].

Do not administer Docetaxel Injection to patients with neutrophil counts of <1500 cells/mm^3. Monitor blood counts frequently as neutropenia may be severe and result in infection [see Warnings and Precautions (5.3)].

Do not administer Docetaxel Injection to patients who have a history of severe hypersensitivity reactions to Docetaxel Injection or to other drugs formulated with polysorbate 80 [see Contraindications (4)]. Severe hypersensitivity reactions have been reported in patients despite dexamethasone premedication. Hypersensitivity reactions require immediate discontinuation of the Docetaxel infusion and administration of appropriate therapy [see Warnings and Precautions (5.5)].

Severe fluid retention occurred in 6.5% (6/92) of patients despite use of dexamethasone premedication. It was characterized by one or more of the following events: poorly tolerated peripheral edema, generalized edema, pleural effusion requiring urgent drainage, dyspnea at rest, cardiac tamponade, or pronounced abdominal distention (due to ascites) [see Warnings and Precautions (5.6)].

1 INDICATIONS AND USAGE

1.1 Breast Cancer

Docetaxel Injection is indicated for the treatment of patients with locally advanced or metastatic breast cancer after failure of prior chemotherapy.

Docetaxel Injection in combination with doxorubicin and cyclophosphamide is indicated for the adjuvant treatment of patients with operable node-positive breast cancer.

1.2 Non-Small Cell Lung Cancer

Docetaxel Injection as a single agent is indicated for the treatment of patients with locally advanced or metastatic non-small cell lung cancer after failure of prior platinum-based chemotherapy.

Docetaxel Injection in combination with cisplatin is indicated for the treatment of patients with unresectable, locally advanced or metastatic non-small cell lung cancer who have not previously received chemotherapy for this condition.

1.3 Prostate Cancer

Docetaxel Injection in combination with prednisone is indicated for the treatment of patients with metastatic castration-resistant prostate cancer.

1.4 Gastric Adenocarcinoma

Docetaxel Injection in combination with cisplatin and fluorouracil is indicated for the treatment of patients with advanced gastric adenocarcinoma, including adenocarcinoma of the gastroesophageal junction, who have not received prior chemotherapy for advanced disease.

1.5 Head and Neck Cancer

Docetaxel Injection in combination with cisplatin and fluorouracil is indicated for the induction treatment of patients with locally advanced squamous cell carcinoma of the head and neck (SCCHN).

2 DOSAGE AND ADMINISTRATION

For all indications, toxicities may warrant dosage adjustments [see Dosage and Administration (2.7)].

Administer in a facility equipped to manage possible complications (e.g. anaphylaxis).

2.1 Breast Cancer

- For locally advanced or metastatic breast cancer after failure of prior chemotherapy, the recommended dose of Docetaxel Injection is 60 mg/m^2 to 100 mg/m^2 administered intravenously over 1 hour every 3 weeks.
- For the adjuvant treatment of operable node-positive breast cancer, the recommended Docetaxel Injection dose is 75 mg/m^2 administered 1 hour after doxorubicin 50 mg/m^2 and cyclophosphamide 500 mg/m^2 every 3 weeks for 6 courses. Prophylactic G-CSF may be used to mitigate the risk of hematological toxicities [see Dosage and Administration (2.7)].

2.2 Non-Small Cell Lung Cancer

- For treatment after failure of prior platinum-based chemotherapy, Docetaxel Injection was evaluated as monotherapy, and the recommended dose is 75 mg/m^2 administered intravenously over 1 hour every 3 weeks. A dose of 100 mg/m^2 in patients previously treated with chemotherapy was associated with increased hematologic toxicity, infection, and treatment-related mortality in randomized controlled trials [see Boxed Warning, Dosage and Administration (2.7), Warnings and Precautions (5), Clinical Studies (14)].
- For chemotherapy-naive patients, Docetaxel Injection was evaluated in combination with cisplatin. The recommended dose of Docetaxel Injection is 75 mg/m^2 administered intravenously over 1 hour immediately followed by cisplatin 75 mg/m^2 over 30 to 60 minutes every 3 weeks [see Dosage and Administration (2.7)].

2.3 Prostate Cancer

- For metastatic castration-resistant prostate cancer, the recommended dose of Docetaxel Injection is 75 mg/m^2 every 3 weeks as a 1 hour intravenous infusion. Prednisone 5 mg orally twice daily is administered continuously [see Dosage and Administration (2.7)].

2.4 Gastric Adenocarcinoma

- For gastric adenocarcinoma, the recommended dose of Docetaxel Injection is 75 mg/m^2 as a 1 hour intravenous infusion, followed by cisplatin 75 mg/m^2, as a 1 to 3 hour intravenous infusion (both on day 1 only), followed by fluorouracil 750 mg/m^2 per day given as a 24-hour continuous intravenous infusion for 5 days, starting at the end of the cisplatin infusion. Treatment is repeated every three weeks. Patients must receive premedication with antiemetics and appropriate hydration for cisplatin administration [see Dosage and Administration (2.7)].

2.5 Head and Neck Cancer

Patients must receive premedication with antiemetics, and appropriate hydration (prior to and after cisplatin administration). Prophylaxis for neutropenic infections should be administered. All patients treated on the Docetaxel Injection containing arms of the TAX323 and TAX324 studies received prophylactic antibiotics.

Induction Chemotherapy Followed by Radiotherapy (TAX323)
For the induction treatment of locally advanced inoperable SCCHN, the recommended dose of Docetaxel Injection is 75 mg/m^2 as a 1 hour intravenous infusion followed by cisplatin 75 mg/m^2 intravenously over 1 hour, on day one, followed by fluorouracil as a continuous intravenous infusion at 750 mg/m^2 per day for five days. This regimen is administered every 3 weeks for 4 cycles. Following chemotherapy, patients should receive radiotherapy [see Dosage and Administration (2.7)].

Induction Chemotherapy Followed by Chemoradiotherapy (TAX324)
For the induction treatment of patients with locally advanced (unresectable, low surgical cure, or organ preservation) SCCHN, the recommended dose of Docetaxel Injection is 75 mg/m^2 as a 1 hour intravenous infusion on day 1, followed by cisplatin 100 mg/m^2 administered as a 30-minute to 3 hour infusion, followed by fluorouracil 1000 mg/m^2/day as a continuous infusion from day 1 to day 4. This regimen is administered every 3 weeks for 3 cycles. Following chemotherapy, patients should receive chemoradiotherapy [see Dosage and Administration (2.7)].

2.6 Premedication Regimen

All patients should be premedicated with oral corticosteroids (see below for prostate cancer) such as dexamethasone 16 mg per day (e.g., 8 mg twice daily) for 3 days starting 1 day prior to Docetaxel Injection administration in order to reduce the incidence and severity of fluid retention as well as the severity of hypersensitivity reactions [see Boxed Warning, Warnings and Precautions (5.5)].

For metastatic castration-resistant prostate cancer, given the concurrent use of prednisone, the recommended premedication regimen is oral dexamethasone 8 mg at 12 hours, 3 hours, and 1 hour before the Docetaxel Injection infusion [see Warnings and Precautions (5.5)].

2.7 Dosage Adjustments During Treatment

Breast Cancer

Patients who are dosed initially at 100 mg/m^2 and who experience either febrile neutropenia, neutrophils <500 cells/mm^3 for more than 1 week, or severe or cumulative cutaneous reactions during Docetaxel Injection therapy should have the dosage adjusted from 100 mg/m^2 to 75 mg/m^2. If the patient continues to experience these reactions, the dosage should either be decreased from 75 mg/m^2 to 55 mg/m^2 or the treatment should be discontinued. Conversely, patients who are dosed initially at 60 mg/m^2 and who do not experience febrile neutropenia, neutrophils <500 cells/mm^3 for more than 1 week, severe or cumulative cutaneous reactions, or severe peripheral neuropathy during Docetaxel Injection therapy may tolerate higher doses. Patients who develop ≥grade 3 peripheral neuropathy should have Docetaxel Injection treatment discontinued entirely.

Combination Therapy with Docetaxel Injection in the Adjuvant Treatment of Breast Cancer

Docetaxel Injection in combination with doxorubicin and cyclophosphamide should be administered when the neutrophil count is ≥1,500 cells/mm^3. Patients who experience febrile neutropenia should receive G-CSF in all subsequent cycles. Patients who continue to experience this reaction should remain on G-CSF and have their Docetaxel Injection dose reduced to 60 mg/m^2. Patients who experience grade 3 or 4 stomatitis should have their Docetaxel Injection dose decreased to 60 mg/m^2. Patients who experience severe or cumulative cutaneous reactions or moderate neurosensory signs and/or symptoms during Docetaxel Injection therapy should have their dosage of Docetaxel Injection reduced from 75 mg/m^2 to 60 mg/m^2. If the patient continues to experience these reactions at 60 mg/m^2, treatment should be discontinued.

Non-Small Cell Lung Cancer

Monotherapy with Docetaxel Injection for NSCLC treatment after failure of prior platinum-based chemotherapy

Patients who are dosed initially at 75 mg/m^2 and who experience either febrile neutropenia, neutrophils <500 cells/mm^3 for more than one week, severe or cumulative cutaneous reactions, or other grade 3/4 non-hematological toxicities during Docetaxel Injection treatment should have treatment withheld until resolution of the toxicity and then resumed at 55 mg/m^2. Patients who develop ≥grade 3 peripheral neuropathy should have Docetaxel Injection treatment discontinued entirely.

Combination therapy with Docetaxel Injection for chemotherapy-naive NSCLC

For patients who are dosed initially at Docetaxel Injection 75 mg/m^2 in combination with cisplatin, and whose nadir of platelet count during the previous course of therapy is <25,000 cells/mm^3, in patients who experience febrile neutropenia, and in patients with serious non-hematologic toxicities, the Docetaxel Injection dosage in subsequent cycles should be reduced to 65 mg/m^2. In patients who require a further dose reduction, a dose of 50 mg/m^2 is recommended. For cisplatin dosage adjustments, see manufacturers’ prescribing information.

Prostate Cancer

Combination therapy with Docetaxel Injection for metastatic castration-resistant prostate cancer

Docetaxel Injection should be administered when the neutrophil count is ≥1,500 cells/mm^3. Patients who experience either febrile neutropenia, neutrophils <500 cells/mm^3 for more than one week, severe or cumulative cutaneous reactions or moderate neurosensory signs and/or symptoms during Docetaxel Injection therapy should have the dosage of Docetaxel Injection reduced from 75 mg/m^2 to 60 mg/m^2. If the patient continues to experience these reactions at 60 mg/m^2, the treatment should be discontinued.

Gastric or Head and Neck Cancer

Docetaxel Injection in combination with cisplatin and fluorouracil in gastric cancer or head and neck cancer

Patients treated with Docetaxel Injection in combination with cisplatin and fluorouracil must receive antiemetics and appropriate hydration according to current institutional guidelines. In both studies, G-CSF was recommended during the second and/or subsequent cycles in case of febrile neutropenia, or documented infection with neutropenia, or neutropenia lasting more than 7 days. If an episode of febrile neutropenia, prolonged neutropenia or neutropenic infection occurs despite G-CSF use, the Docetaxel Injection dose should be reduced from 75 mg/m^2 to 60 mg/m^2. If subsequent episodes of complicated neutropenia occur the Docetaxel Injection dose should be reduced from 60 mg/m^2 to 45 mg/m^2. In case of grade 4 thrombocytopenia the Docetaxel Injection dose should be reduced from 75 mg/m^2 to 60 mg/m^2. Do not retreat patients with subsequent cycles of Docetaxel Injection until neutrophils recover to a level >1,500 cells/mm^3 [see Contraindications (4)]. Avoid retreating patients until platelets recover to a level >100,000 cells/mm^3. Discontinue treatment if these toxicities persist [see Warnings and Precautions (5.3)].

Recommended dose modifications for toxicities in patients treated with Docetaxel Injection in combination with cisplatin and fluorouracil are shown in Table 1.

Table 1 - Recommended Dose Modifications for Toxicities in Patients Treated with Docetaxel Injection in Combination with Cisplatin and Fluorouracil
Toxicity | Dosage adjustment
Diarrhea grade 3 | First episode: reduce fluorouracil dose by 20%. Second episode: then reduce Docetaxel Injection dose by 20%.
Diarrhea grade 4 | First episode: reduce Docetaxel Injection and fluorouracil doses by 20%. Second episode: discontinue treatment.
Stomatitis/mucositis grade 3 | First episode: reduce fluorouracil dose by 20%. Second episode: stop fluorouracil only, at all subsequent cycles. Third episode: reduce Docetaxel Injection dose by 20%.
Stomatitis/mucositis grade 4 | First episode: stop fluorouracil only, at all subsequent cycles. Second episode: reduce Docetaxel Injection dose by 20%.

Liver dysfunction: In case of AST/ALT >2.5 to ≤5 x ULN and AP ≤2.5 x ULN, or AST/ALT >1.5 to ≤5 x ULN and AP >2.5 to ≤5 x ULN, Docetaxel Injection should be reduced by 20%.

In case of AST/ALT >5 x ULN and/or AP >5 x ULN Docetaxel Injection should be stopped.

The dose modifications for cisplatin and fluorouracil in the gastric cancer study are provided below.

Cisplatin dose modifications and delays

Peripheral neuropathy: A neurological examination should be performed before entry into the study, and then at least every 2 cycles and at the end of treatment. In the case of neurological signs or symptoms, more frequent examinations should be performed and the following dose modifications can be made according to NCI-CTCAE grade:

- Grade 2: Reduce cisplatin dose by 20%.
- Grade 3: Discontinue treatment.

Ototoxicity: In the case of grade 3 toxicity, discontinue treatment.

Nephrotoxicity: In the event of a rise in serum creatinine ≥grade 2 (>1.5 x normal value) despite adequate rehydration, CrCl should be determined before each subsequent cycle and the following dose reductions should be considered (see Table 2).

For other cisplatin dosage adjustments, also refer to the manufacturers’ prescribing information.

Table 2 - Dose Reductions for Evaluation of Creatinine Clearance
Creatinine clearance result before next cycle | Cisplatin dose next cycle
CrCl ≥60 mL/min | Full dose of cisplatin was given. CrCl was to be repeated before each treatment cycle.
 | Dose of cisplatin was reduced by 50% at subsequent cycle. If CrCl was
CrCl between 40 and 59 mL/min | >60 mL/min at end of cycle, full cisplatin dose was reinstituted at the next cycle.
 | If no recovery was observed, then cisplatin was omitted from the next treatment cycle.
 | Dose of cisplatin was omitted in that treatment cycle only.
 | If CrCl was still <40 mL/min at the end of cycle, cisplatin was discontinued.
CrCl <40 mL/min | If CrCl was >40 and <60 mL/min at end of cycle, a 50% cisplatin dose was given at the next cycle.
 | If CrCl was >60 mL/min at end of cycle, full cisplatin dose was given at next cycle.
CrCl = Creatinine clearance

Fluorouracil dose modifications and treatment delays

For diarrhea and stomatitis, see Table 1.

In the event of grade 2 or greater plantar-palmar toxicity, fluorouracil should be stopped until recovery. The fluorouracil dosage should be reduced by 20%.

For other greater than grade 3 toxicities, except alopecia and anemia, chemotherapy should be delayed (for a maximum of 2 weeks from the planned date of infusion) until resolution to grade ≤1 and then recommenced, if medically appropriate.

For other fluorouracil dosage adjustments, also refer to the manufacturers’ prescribing information.

Combination Therapy with Strong CYP3A4 Inhibitors

Avoid using concomitant strong CYP3A4 inhibitors (e.g., ketoconazole, itraconazole, clarithromycin, atazanavir, indinavir, nefazodone, nelfinavir, ritonavir, saquinavir, telithromycin and voriconazole). There are no clinical data with a dose adjustment in patients receiving strong CYP3A4 inhibitors. Based on extrapolation from a pharmacokinetic study with ketoconazole in 7 patients, consider a 50% docetaxel dose reduction if patients require coadministration of a strong CYP3A4 inhibitor [see Drug Interactions (7), Clinical Pharmacology (12.3)].

2.8 Administration Precautions

Docetaxel Injection is a hazardous anticancer drug and, as with other potentially toxic compounds, caution should be exercised when handling and preparing Docetaxel Injection solutions. The use of gloves is recommended [see How Supplied/Storage and Handling (16.3)].

If Docetaxel Injection initial diluted solution, or final dilution for infusion should come into contact with the skin, immediately and thoroughly wash with soap and water. If Docetaxel Injection initial diluted solution, or final dilution for infusion should come into contact with mucosa, immediately and thoroughly wash with water.

Contact of the Docetaxel Injection with plasticized PVC equipment or devices used to prepare solutions for infusion is not recommended. In order to minimize patient exposure to the plasticizer DEHP (di-2-ethylhexyl phthalate), which may be leached from PVC infusion bags or sets, the final Docetaxel Injection dilution for infusion should be stored in bottles (glass, polypropylene) or plastic bags (polypropylene, polyolefin) and administered through polyethylene-lined administration sets.

One-vial Docetaxel Injection

Docetaxel Injection requires NO prior dilution with a diluent and is ready to add to the infusion solution.

Please follow the preparation instructions provided below.

2.9 Preparation and Administration

DO NOT use the two-vial formulation (Injection and diluent) with the one-vial formulation.

One-vial Docetaxel Injection

Docetaxel Injection (20 mg/mL) requires NO prior dilution with a diluent and is ready to add to the infusion solution. Use only a 21 gauge needle to withdraw Docetaxel Injection from the vial because larger bore needles (e.g., 18 and 19 gauge) may result in stopper coring and rubber particulates.

1. Docetaxel Injection vials should be stored at 25°C (77°F); excursions permitted to 15° to 30°C (59° to 86°F) protected from light.
2. Using only a 21 gauge needle, aseptically withdraw the required amount of Docetaxel Injection
  (20 mg docetaxel/mL) with a calibrated syringe and inject via a single injection (one shot) into a 250 mL infusion bag or bottle of either 0.9% Sodium Chloride solution or 5% Dextrose solution to produce a final concentration of 0.3 mg/mL to 0.74 mg/mL. If a dose greater than 200 mg of Docetaxel Injection is required, use a larger volume of the infusion vehicle so that a concentration of 0.74 mg/mL Docetaxel Injection is not exceeded.
3. Thoroughly mix the infusion by gentle manual rotation.
4. As with all parenteral products, Docetaxel Injection should be inspected visually for particulate matter or discoloration prior to administration whenever the solution and container permit. If the Docetaxel Injection dilution for intravenous infusion is not clear or appears to have precipitation, it should be discarded.
5. Docetaxel Injection infusion solution is supersaturated, therefore may crystallize over time. If crystals appear, the solution must no longer be used and shall be discarded.
  The Docetaxel Injection dilution for infusion should be administered intravenously as a 1-hour infusion under ambient room temperature (below 25°C) and lighting conditions.

2.10 Stability

Docetaxel Injection final dilution for infusion, if stored between 2°C and 25°C (36°F and 77°F) is stable for 6 hours. Docetaxel Injection final dilution for infusion (in either 0.9% Sodium Chloride solution or 5% Dextrose solution) should be used within 6 hours (including the 1 hour intravenous administration).

In addition, physical and chemical in-use stability of the infusion solution prepared as recommended has been demonstrated in non-PVC bags up to 48 hours when stored between 2°C and 8°C (36°F and 46°F).

3 DOSAGE FORMS AND STRENGTHS

One-vial Docetaxel Injection, USP

Docetaxel Injection, USP is available as 20 mg/mL and 80 mg/4 mL, in single-dose vials.

4 CONTRAINDICATIONS

Docetaxel Injection is contraindicated in patients with:

- neutrophil counts of <1500 cells/mm^3 [see Warnings and Precautions (5.3)].
- a history of severe hypersensitivity reactions to docetaxel or to other drugs formulated with polysorbate 80. Severe reactions, including anaphylaxis, have occurred [see Warnings and Precautions (5.5)].

5 WARNINGS AND PRECAUTIONS

5.1 Toxic Deaths

Breast Cancer

Docetaxel Injection administered at 100 mg/m^2 was associated with deaths considered possibly or probably related to treatment in 2.0% (19/965) of metastatic breast cancer patients, both previously treated and untreated, with normal baseline liver function and in 11.5% (7/61) of patients with various tumor types who had abnormal baseline liver function (AST and/or ALT >1.5 times ULN together with AP >2.5 times ULN). Among patients dosed at 60 mg/m^2, mortality related to treatment occurred in 0.6% (3/481) of patients with normal liver function, and in 3 of 7 patients with abnormal liver function. Approximately half of these deaths occurred during the first cycle. Sepsis accounted for the majority of the deaths.

Non-Small Cell Lung Cancer

Docetaxel Injection administered at a dose of 100 mg/m^2 in patients with locally advanced or metastatic non-small cell lung cancer who had a history of prior platinum-based chemotherapy was associated with increased treatment-related mortality (14% and 5% in two randomized, controlled studies). There were 2.8% treatment-related deaths among the 176 patients treated at the 75 mg/m^2 dose in the randomized trials. Among patients who experienced treatment-related mortality at the 75 mg/m^2 dose level, 3 of 5 patients had an ECOG PS of 2 at study entry [see Dosage and Administration (2.2), Clinical Studies (14)].

5.2 Hepatic Impairment

Patients with elevations of bilirubin or abnormalities of transaminase concurrent with alkaline phosphatase are at increased risk for the development of severe neutropenia, febrile neutropenia, infections, severe thrombocytopenia, severe stomatitis, severe skin toxicity, and toxic death.

Avoid Docetaxel Injection in patients with bilirubin > upper limit of normal (ULN), or to patients with AST and/or ALT >1.5 × ULN concomitant with alkaline phosphatase >2.5 × ULN [see Warnings and Precautions (5.1)].

For patients with isolated elevations of transaminase >1.5 × ULN, consider Docetaxel Injection dose modifications [see Dosage and Administration (2.7)].

Measure bilirubin, AST or ALT, and alkaline phosphatase prior to each cycle of Docetaxel Injection therapy.

5.3 Hematologic Effects

Perform frequent peripheral blood cell counts on all patients receiving Docetaxel Injection. Do not retreat patients with subsequent cycles of Docetaxel Injection until neutrophils recover to a level >1500 cells/mm^3 [see Contraindications (4)]. Avoid retreating patients until platelets recover to a level >100,000 cells/mm^3.

A 25% reduction in the dose of Docetaxel Injection is recommended during subsequent cycles following severe neutropenia (<500 cells/mm^3) lasting 7 days or more, febrile neutropenia, or a grade 4 infection in a Docetaxel Injection cycle [see Dosage and Administration (2.7)].

Neutropenia (<2000 neutrophils/mm^3) occurs in virtually all patients given 60 mg/m^2 to 100 mg/m^2 of Docetaxel Injection and grade 4 neutropenia (<500 cells/mm^3) occurs in 85% of patients given 100 mg/m^2 and 75% of patients given 60 mg/m^2. Frequent monitoring of blood counts is, therefore, essential so that dose can be adjusted. Docetaxel Injection should not be administered to patients with neutrophils <1500 cells/mm^3.

Febrile neutropenia occurred in about 12% of patients given 100 mg/m^2 but was very uncommon in patients given 60 mg/m^2. Hematologic responses, febrile reactions and infections, and rates of septic death for different regimens are dose related [see Adverse Reactions (6.1), Clinical Studies (14)].

Three breast cancer patients with severe liver impairment (bilirubin >1.7 times ULN) developed fatal gastrointestinal bleeding associated with severe drug-induced thrombocytopenia. In gastric cancer patients treated with docetaxel in combination with cisplatin and fluorouracil (TCF), febrile neutropenia and/or neutropenic infection occurred in 12% of patients receiving G-CSF compared to 28% who did not. Patients receiving TCF should be closely monitored during the first and subsequent cycles for febrile neutropenia and neutropenic infection [see Dosage and Administration (2.7), Adverse Reactions (6)].

5.4 Enterocolitis and Neutropenic Colitis

Enterocolitis and neutropenic colitis (typhlitis) have occurred in patients treated with Docetaxel Injection alone and in combination with other chemotherapeutic agents, despite the co-administration of G-CSF. Caution is recommended for patients with neutropenia, particularly at risk for developing gastrointestinal complications. Enterocolitis and neutropenic enterocolitis may develop at any time, and could lead to death as early as the first day of symptom onset. Monitor patients closely from onset of any symptoms of gastrointestinal toxicity. Inform patients to contact their healthcare provider with new, or worsening symptoms of gastrointestinal toxicity [see Dosage and Administration (2), Warnings and Precautions (5.3), Adverse Reactions (6.2)].

5.5 Hypersensitivity Reactions

Monitor patients closely for hypersensitivity reactions, especially during the first and second infusions. Severe hypersensitivity reactions characterized by generalized rash/erythema, hypotension and/or bronchospasm, or fatal anaphylaxis, have been reported in patients pre-medicated with 3 days of corticosteroids. Severe hypersensitivity reactions require immediate discontinuation of the Docetaxel Injection infusion and aggressive therapy. Do not rechallenge patients with a history of severe hypersensitivity reactions with Docetaxel Injection [see Contraindications (4)].

Patients who have previously experienced a hypersensitivity reaction to paclitaxel may develop a hypersensitivity reaction to docetaxel that may include severe or fatal reactions such as anaphylaxis. Monitor patients with a previous history of hypersensitivity to paclitaxel closely during initiation of Docetaxel Injection therapy. Hypersensitivity reactions may occur within a few minutes following initiation of a Docetaxel Injection infusion. If minor reactions such as flushing or localized skin reactions occur, interruption of therapy is not required. All patients should be premedicated with an oral corticosteroid prior to the initiation of the infusion of Docetaxel Injection [see Dosage and Administration (2.6)].

5.6 Fluid Retention

Severe fluid retention has been reported following Docetaxel Injection therapy. Patients should be premedicated with oral corticosteroids prior to each Docetaxel Injection administration to reduce the incidence and severity of fluid retention [see Dosage and Administration (2.6)]. Patients with pre-existing effusions should be closely monitored from the first dose for the possible exacerbation of the effusions.

When fluid retention occurs, peripheral edema usually starts in the lower extremities and may become generalized with a median weight gain of 2 kg.

Among 92 breast cancer patients premedicated with 3-day corticosteroids, moderate fluid retention occurred in 27.2% and severe fluid retention in 6.5%. The median cumulative dose to onset of moderate or severe fluid retention was 819 mg/m^2. Nine of 92 patients (9.8%) of patients discontinued treatment due to fluid retention: 4 patients discontinued with severe fluid retention; the remaining 5 had mild or moderate fluid retention. The median cumulative dose to treatment discontinuation due to fluid retention was 1021 mg/m^2. Fluid retention was completely, but sometimes slowly, reversible with a median of 16 weeks from the last infusion of Docetaxel Injection to resolution (range: 0 to 42+ weeks). Patients developing peripheral edema may be treated with standard measures, e.g., salt restriction, oral diuretic(s).

5.7 Second Primary Malignancies

Second primary malignancies, notably acute myeloid leukemia (AML), myelodysplastic syndrome (MDS), Non-Hodgkin’s Lymphoma (NHL), and renal cancer, have been reported in patients treated with docetaxel-containing regimens. These adverse reactions may occur several months or years after docetaxel-containing therapy.

Treatment-related AML or MDS has occurred in patients given anthracyclines and/or cyclophosphamide, including use in adjuvant therapy for breast cancer. In the adjuvant breast cancer trial (TAX316) AML occurred in 3 of 744 patients who received Docetaxel Injection, doxorubicin and cyclophosphamide (TAC) and in 1 of 736 patients who received fluorouracil, doxorubicin, and cyclophosphamide [see Clinical Studies (14.2)]. In TAC-treated patients, the risk of delayed myelodysplasia or myeloid leukemia requires hematological follow-up. Monitor patients for second primary malignancies [see Adverse Reactions (6.1)].

5.8 Cutaneous Reactions

Localized erythema of the extremities with edema followed by desquamation has been observed. In case of severe skin toxicity, an adjustment in dosage is recommended [see Dosage and Administration (2.7)]. The discontinuation rate due to skin toxicity was 1.6% (15/965) for metastatic breast cancer patients. Among 92 breast cancer patients premedicated with 3-day corticosteroids, there were no cases of severe skin toxicity reported and no patient discontinued Docetaxel Injection due to skin toxicity.

Severe cutaneous adverse reactions (SCARs) such as Stevens-Johnson syndrome (SJS), toxic epidermal necrolysis (TEN), and acute generalized exanthematous pustulosis (AGEP) have been reported in association with docetaxel treatment. Patients should be informed about the signs and symptoms of serious skin manifestations and monitored closely. Permanent treatment discontinuation should be considered in patients who experience SCARs.

5.9 Neurologic Reactions

Severe neurosensory symptoms (e.g. paresthesia, dysesthesia, pain) were observed in 5.5% (53/965) of metastatic breast cancer patients, and resulted in treatment discontinuation in 6.1%. When these symptoms occur, dosage must be adjusted. If symptoms persist, treatment should be discontinued [see Dosage and Administration (2.7)]. Patients who experienced neurotoxicity in clinical trials and for whom follow-up information on the complete resolution of the event was available had spontaneous reversal of symptoms with a median of 9 weeks from onset (range: 0 to 106 weeks). Severe peripheral motor neuropathy mainly manifested as distal extremity weakness occurred in 4.4% (42/965).

5.10 Eye Disorders

Cystoid macular edema (CME) has been reported in patients treated with Docetaxel Injection. Patients with impaired vision should undergo a prompt and comprehensive ophthalmologic examination. If CME is diagnosed, Docetaxel Injection treatment should be discontinued and appropriate treatment initiated. Alternative non-taxane cancer treatment should be considered.

5.11 Asthenia

Severe asthenia has been reported in 14.9% (144/965) of metastatic breast cancer patients but has led to treatment discontinuation in only 1.8%. Symptoms of fatigue and weakness may last a few days up to several weeks and may be associated with deterioration of performance status in patients with progressive disease.

5.12 Embryo-Fetal Toxicity

Based on findings from animal reproduction studies and its mechanism of action, Docetaxel Injection can cause fetal harm when administered to a pregnant woman [see Clinical Pharmacology (12.1)]. Available data from case reports in the literature and pharmacovigilance with docetaxel use in pregnant women are not sufficient to inform the drug-associated risk of major birth defects, miscarriage or adverse maternal or fetal outcomes. In animal reproduction studies, administration of docetaxel to pregnant rats and rabbits during the period of organogenesis caused embryo-fetal toxicities, including intrauterine mortality, at doses as low as 0.02 and 0.003 times the recommended human dose based on body surface area, respectively.

Advise pregnant women and females of reproductive potential of the potential risk to a fetus.

Verify pregnancy status in females of reproductive potential prior to initiating Docetaxel Injection. Advise females of reproductive potential to use effective contraception during treatment and for 2 months after the last dose of Docetaxel Injection. Advise male patients with female partners of reproductive potential to use effective contraception during treatment and for 4 months after the last dose of Docetaxel Injection [see Use in Specific Populations (8.1, 8.3)].

5.13 Alcohol Content

Cases of intoxication have been reported with some formulations of docetaxel due to the alcohol content. The alcohol content in a dose of Docetaxel Injection may affect the central nervous system and should be taken into account for patients in whom alcohol intake should be avoided or minimized. Consideration should be given to the alcohol content in Docetaxel Injection on the ability to drive or use machines immediately after the infusion. Each administration of Docetaxel Injection at 100 mg/m^2 delivers 2.0 g/m^2 of ethanol. For a patient with a BSA of 2.0 m^2, this would deliver 4.0 grams of ethanol [see Description (11)]. Other docetaxel products may have a different amount of alcohol.

5.14 Tumor Lysis Syndrome

Tumor lysis syndrome has been reported with docetaxel [see Adverse Reactions (6.2)]. Patients at risk of tumor lysis syndrome (e.g., with renal impairment, hyperuricemia, bulky tumor) should be closely monitored prior to initiating Docetaxel Injection and periodically during treatment. Correction of dehydration and treatment of high uric acid levels are recommended prior to initiation of treatment.

6 ADVERSE REACTIONS

The most serious adverse reactions from Docetaxel Injection are:

- Toxic Deaths [see Boxed Warning, Warnings and Precautions (5.1)]
- Hepatic Impairment [see Boxed Warning, Warnings and Precautions (5.2)]
- Hematologic Effects [see Boxed Warning, Warnings and Precautions (5.3)]
- Enterocolitis and Neutropenic Colitis [see Warnings and Precautions (5.4)]
- Hypersensitivity Reactions [see Boxed Warning, Warnings and Precautions (5.5)]
- Fluid Retention [see Boxed Warning, Warnings and Precautions (5.6)]
- Second Primary Malignancies [see Warnings and Precautions (5.7)]
- Cutaneous Reactions [see Warnings and Precautions (5.8)]
- Neurologic Reactions [see Warnings and Precautions (5.9)]
- Eye Disorders [see Warnings and Precautions (5.10)]
- Asthenia [see Warnings and Precautions (5.11)]
- Alcohol Content [see Warnings and Precautions (5.13)]

The most common adverse reactions across all Docetaxel Injection indications are infections, neutropenia, anemia, febrile neutropenia, hypersensitivity, thrombocytopenia, neuropathy, dysgeusia, dyspnea, constipation, anorexia, nail disorders, fluid retention, asthenia, pain, nausea, diarrhea, vomiting, mucositis, alopecia, skin reactions, and myalgia. Incidence varies depending on the indication.

Adverse reactions are described according to indication. Because clinical trials are conducted under widely varying conditions, adverse reaction rates observed in the clinical trials of a drug cannot be directly compared to rates in the clinical trials of another drug and may not reflect the rates observed in practice.

Responding patients may not experience an improvement in performance status on therapy and may experience worsening. The relationship between changes in performance status, response to therapy, and treatment-related side effects has not been established.

6.1 Clinical Trials Experience

Breast Cancer

Monotherapy with Docetaxel Injection for locally advanced or metastatic breast cancer after failure of prior chemotherapy

Docetaxel Injection 100 mg/m^2: Adverse drug reactions occurring in at least 5% of patients are compared for three populations who received Docetaxel Injection administered at 100 mg/m^2 as a 1-hour infusion every 3 weeks: 2045 patients with various tumor types and normal baseline liver function tests; the subset of 965 patients with locally advanced or metastatic breast cancer, both previously treated and untreated with chemotherapy, who had normal baseline liver function tests; and an additional 61 patients with various tumor types who had abnormal liver function tests at baseline. These reactions were described using COSTART terms and were considered possibly or probably related to Docetaxel Injection. At least 95% of these patients did not receive hematopoietic support. The safety profile is generally similar in patients receiving Docetaxel Injection for the treatment of breast cancer and in patients with other tumor types (see Table 3).

Table 3 - Summary of Adverse Reactions in Patients Receiving Docetaxel Injection at 100 mg/m^2
 | All Tumor Types | All Tumor Types | Breast Cancer
 | Normal LFTs* | Elevated LFTs** | Normal LFTs*
Adverse Reaction | n=2045 | n=61 | n=965
 | % | % | %
Hematologic
Neutropenia
<2000 cells/mm^3 | 96 | 96 | 99
<500 cells/mm^3 | 75 | 88 | 86
Leukopenia
<4000 cells/mm^3 | 96 | 98 | 99
<1000 cells/mm^3 | 32 | 47 | 44
Thrombocytopenia
<100,000 cells/mm^3 | 8 | 25 | 9
Anemia
<11 g/dL | 90 | 92 | 94
<8 g/dL | 9 | 31 | 8
Febrile Neutropenia*** | 11 | 26 | 12
Septic Death | 2 | 5 | 1
Non-Septic Death | 1 | 7 | 1
Infections
Any | 22 | 33 | 22
Severe | 6 | 16 | 6
Fever in Absence of Infection
Any | 31 | 41 | 35
Severe | 2 | 8 | 2
Hypersensitivity Reactions
Regardless of Premedication
Any | 21 | 20 | 18
Severe | 4 | 10 | 3
With 3-day Premedication | n=92 | n=3 | n=92
Any | 15 | 33 | 15
Severe | 2 | 0 | 2
Fluid Retention
Regardless of Premedication
Any | 47 | 39 | 60
Severe | 7 | 8 | 9
With 3-day Premedication | n=92 | n=3 | n=92
Any | 64 | 67 | 64
Severe | 7 | 33 | 7
Neurosensory
Any | 49 | 34 | 58
Severe | 4 | 0 | 6
Cutaneous
Any | 48 | 54 | 47
Severe | 5 | 10 | 5
Nail Changes
Any | 31 | 23 | 41
Severe | 3 | 5 | 4
Gastrointestinal
Nausea | 39 | 38 | 42
Vomiting | 22 | 23 | 23
Diarrhea | 39 | 33 | 43
Severe | 5 | 5 | 6
Stomatitis
Any | 42 | 49 | 52
Severe | 6 | 13 | 7
Alopecia | 76 | 62 | 74
Asthenia
Any | 62 | 53 | 66
Severe | 13 | 25 | 15
Myalgia
Any | 19 | 16 | 21
Severe | 2 | 2 | 2
Arthralgia | 9 | 7 | 8
Infusion Site Reactions | 4 | 3 | 4
*Normal Baseline LFTs: Transaminases ≤1.5 times ULN or alkaline phosphatase ≤2.5 times ULN or isolated elevations of transaminases or alkaline phosphatase up to 5 times ULN
**Elevated Baseline LFTs: AST and/or ALT >1.5 times ULN concurrent with alkaline phosphatase >2.5 times ULN
***Febrile Neutropenia: ANC grade 4 with fever >38°C with intravenous antibiotics and/or hospitalization

Hematologic Reactions

Reversible marrow suppression was the major dose-limiting toxicity of Docetaxel Injection [see Warnings and Precautions (5.3)]. The median time to nadir was 7 days, while the median duration of severe neutropenia (<500 cells/mm^3) was 7 days. Among 2045 patients with solid tumors and normal baseline LFTs, severe neutropenia occurred in 75.4% and lasted for more than 7 days in 2.9% of cycles.

Febrile neutropenia (<500 cells/mm^3 with fever >38°C with intravenous antibiotics and/or hospitalization) occurred in 11% of patients with solid tumors, in 12.3% of patients with metastatic breast cancer, and in 9.8% of 92 breast cancer patients premedicated with 3-day corticosteroids.

Severe infectious episodes occurred in 6.1% of patients with solid tumors, in 6.4% of patients with metastatic breast cancer, and in 5.4% of 92 breast cancer patients premedicated with 3-day corticosteroids.

Thrombocytopenia (<100,000 cells/mm^3) associated with fatal gastrointestinal hemorrhage has been reported.

Hypersensitivity Reactions

Severe hypersensitivity reactions have been reported [see Boxed Warning, Warnings and Precautions (5.5)]. Minor events, including flushing, rash with or without pruritus, chest tightness, back pain, dyspnea, drug fever, or chills, have been reported and resolved after discontinuing the infusion and instituting appropriate therapy.

Fluid Retention

Fluid retention can occur with the use of Docetaxel Injection [see Boxed Warning, Dosage and Administration (2.6), Warnings and Precautions (5.6)].

Cutaneous Reactions

Severe skin toxicity is discussed elsewhere in the label [see Warnings and Precautions (5.8)]. Reversible cutaneous reactions characterized by a rash including localized eruptions, mainly on the feet and/or hands, but also on the arms, face, or thorax, usually associated with pruritus, have been observed. Eruptions generally occurred within 1 week after Docetaxel Injection infusion, recovered before the next infusion, and were not disabling.

Severe nail disorders were characterized by hypo or hyperpigmentation, and occasionally by onycholysis (in 0.8% of patients with solid tumors) and pain.

Neurologic Reactions

Neurologic reactions are discussed elsewhere in the label [see Warnings and Precautions (5.9)].

Gastrointestinal Reactions

Nausea, vomiting, and diarrhea were generally mild to moderate. Severe reactions occurred in 3 to 5% of patients with solid tumors and to a similar extent among metastatic breast cancer patients. The incidence of severe reactions was 1% or less for the 92 breast cancer patients premedicated with 3-day corticosteroids.

Severe stomatitis occurred in 5.5% of patients with solid tumors, in 7.4% of patients with metastatic breast cancer, and in 1.1% of the 92 breast cancer patients premedicated with 3-day corticosteroids.

Cardiovascular Reactions

Hypotension occurred in 2.8% of patients with solid tumors; 1.2% required treatment. Clinically meaningful events such as heart failure, sinus tachycardia, atrial flutter, dysrhythmia, unstable angina, pulmonary edema, and hypertension have occurred. Seven of 86 (8.1%) of metastatic breast cancer patients receiving Docetaxel Injection 100 mg/m^2 in a randomized trial and who had serial left ventricular ejection fractions assessed developed deterioration of LVEF by ≥10% associated with a drop below the institutional lower limit of normal.

Infusion Site Reactions

Infusion site reactions were generally mild and consisted of hyperpigmentation, inflammation, redness or dryness of the skin, phlebitis, extravasation, or swelling of the vein.

Hepatic Reactions

In patients with normal LFTs at baseline, bilirubin values greater than the ULN occurred in 8.9% of patients. Increases in AST or ALT >1.5 times the ULN, or alkaline phosphatase >2.5 times ULN, were observed in 18.9% and 7.3% of patients, respectively. While on Docetaxel Injection, increases in AST and/or ALT >1.5 times ULN concomitant with alkaline phosphatase >2.5 times ULN occurred in 4.3% of patients with normal LFTs at baseline. Whether these changes were related to the drug or underlying disease has not been established.

Hematologic and Other Toxicity: Relation to dose and baseline liver chemistry abnormalities

Hematologic and other toxicity is increased at higher doses and in patients with elevated baseline liver function tests (LFTs). In the following tables, adverse drug reactions are compared for three populations: 730 patients with normal LFTs given Docetaxel Injection at 100 mg/m^2 in the randomized and single arm studies of metastatic breast cancer after failure of previous chemotherapy; 18 patients in these studies who had abnormal baseline LFTs (defined as AST and/or ALT >1.5 times ULN concurrent with alkaline phosphatase >2.5 times ULN); and 174 patients in Japanese studies given Docetaxel Injection at 60 mg/m^2 who had normal LFTs (see Tables 4 and 5).

Table 4 - Hematologic Adverse Reactions in Breast Cancer Patients Previously Treated with Chemotherapy Treated at Docetaxel Injection 100 mg/m^2 with Normal or Elevated Liver Function Tests or 60 mg/m^2 with Normal Liver Function Tests
 | Docetaxel Injection |  | Docetaxel Injection
 | 100 mg/m^2 |  | 60 mg/m^2
 | Normal LFTs* | Elevated LFTs** | Normal LFTs*
Adverse Reaction | n=730 | n=18 | n=174
 | % | % | %
Neutropenia
Any <2000 cells/mm^3 | 98 | 100 | 95
Grade 4 <500 cells/mm^3 | 84 | 94 | 75
Thrombocytopenia
Any <100,000 cells/mm^3 | 11 | 44 | 14
Grade 4 <20,000 cells/mm^3 | 1 | 17 | 1
Anemia <11 g/dL | 95 | 94 | 65
Infection***
Any | 23 | 39 | 1
Grade 3 and 4 | 7 | 33 | 0
Febrile Neutropenia****
By Patient | 12 | 33 | 0
By Course | 2 | 9 | 0
Septic Death | 2 | 6 | 1
Non-Septic Death | 1 | 11 | 0
*Normal Baseline LFTs: Transaminases ≤1.5 times ULN or alkaline phosphatase ≤2.5 times ULN or isolated elevations of transaminases or alkaline phosphatase up to 5 times ULN
**Elevated Baseline LFTs: AST and/or ALT >1.5 times ULN concurrent with alkaline phosphatase >2.5 times ULN
***Incidence of infection requiring hospitalization and/or intravenous antibiotics was 8.5% (n=62) among the 730 patients with normal LFTs at baseline; 7 patients had concurrent grade 3 neutropenia, and 46 patients had grade 4 neutropenia.
****Febrile Neutropenia: For 100 mg/m^2, ANC grade 4 and fever >38°C with intravenous antibiotics and/or hospitalization; for 60 mg/m^2, ANC grade 3/4 and fever >38.1°C

Table 5 - Non-Hematologic Adverse Reactions in Breast Cancer Patients Previously Treated with Chemotherapy Treated at Docetaxel Injection 100 mg/m^2 with Normal or Elevated Liver Function Tests or 60 mg/m^2 with Normal Liver Function Tests
 | Docetaxel Injection |  | Docetaxel Injection
 | 100 mg/m^2 |  | 60 mg/m^2
 | Normal LFTs* | Elevated LFTs** | Normal LFTs*
Adverse Reaction | n=730 | n=18 | n=174
 | % | % | %
Acute Hypersensitivity
Reaction Regardless of
Premedication
Any | 13 | 6 | 1
Severe | 1 | 0 | 0
Fluid Retention***
Regardless of Premedication
Any | 56 | 61 | 13
Severe | 8 | 17 | 0
Neurosensory
Any | 57 | 50 | 20
Severe | 6 | 0 | 0
Myalgia | 23 | 33 | 3
Cutaneous
Any | 45 | 61 | 31
Severe | 5 | 17 | 0
Asthenia
Any | 65 | 44 | 66
Severe | 17 | 22 | 0
Diarrhea
Any | 42 | 28 | NA
Severe | 6 | 11
Stomatitis
Any | 53 | 67 | 19
Severe | 8 | 39 | 1
*Normal Baseline LFTs: Transaminases ≤1.5 times ULN or alkaline phosphatase ≤2.5 times ULN or isolated elevations of transaminases or alkaline phosphatase up to 5 times ULN
** Elevated Baseline Liver Function: AST and/or ALT >1.5 times ULN concurrent with alkaline phosphatase >2.5 times ULN
***Fluid Retention includes (by COSTART): edema (peripheral, localized, generalized, lymphedema, pulmonary edema, and edema otherwise not specified) and effusion (pleural, pericardial, and ascites); no premedication given with the 60 mg/m^2 dose
NA = not available

In the three-arm monotherapy trial, TAX313, which compared Docetaxel Injection 60 mg/m^2, 75 mg/m^2 and 100 mg/m^2 in advanced breast cancer, grade 3/4 or severe adverse reactions occurred in 49.0% of patients treated with Docetaxel Injection 60 mg/m^2 compared to 55.3% and 65.9% treated with 75 mg/m^2 and 100 mg/m^2, respectively. Discontinuation due to adverse reactions was reported in 5.3% of patients treated with 60 mg/m^2 versus 6.9% and 16.5% for patients treated at 75 and 100 mg/m^2, respectively. Deaths within 30 days of last treatment occurred in 4.0% of patients treated with 60 mg/m^2 compared to 5.3% and 1.6% for patients treated at 75 mg/m^2 and 100 mg/m^2, respectively.

The following adverse reactions were associated with increasing docetaxel doses: fluid retention (26%, 38%, and 46% at 60 mg/m^2, 75 mg/m^2, and 100 mg/m^2, respectively), thrombocytopenia (7%, 11% and 12%, respectively), neutropenia (92%, 94%, and 97% respectively), febrile neutropenia (5%, 7%, and 14%, respectively), treatment-related grade 3/4 infection (2%, 3%, and 7%, respectively) and anemia (87%, 94%, and 97%, respectively).

Combination therapy with Docetaxel Injection in the adjuvant treatment of breast cancer

The following table presents treatment-emergent adverse reactions observed in 744 patients, who were treated with Docetaxel Injection 75 mg/m^2 every 3 weeks in combination with doxorubicin and cyclophosphamide (see Table 6).

Table 6 - Clinically Important Treatment-Emergent Adverse Reactions Regardless of Causal Relationship in Patients Receiving Docetaxel Injection in Combination with Doxorubicin and Cyclophosphamide (TAX316).
 | Docetaxel Injection 75 mg/m^2+ |  | Fluorouracil 500 mg/m^2+
 | Doxorubicin 50 mg/m^2+ |  | Doxorubicin 50 mg/m^2+
 | Cyclophosphamide 500 mg/m^2 (TAC) |  | Cyclophosphamide 500 mg/m^2 (FAC)
 | n=744 % |  | n=736 %
Adverse Reaction | Any | Grade 3/4 | Any | Grade 3/4
Anemia | 92 | 4 | 72 | 2
Neutropenia | 71 | 66 | 82 | 49
Fever in absence of infection | 47 | 1 | 17 | 0
Infection | 39 | 4 | 36 | 2
Thrombocytopenia | 39 | 2 | 28 | 1
Febrile neutropenia | 25 | N/A | 3 | N/A
Neutropenic infection | 12 | N/A | 6 | N/A
Hypersensitivity reactions | 13 | 1 | 4 | 0
Lymphedema | 4 | 0 | 1 | 0
Fluid Retention* | 35 | 1 | 15 | 0
Peripheral edema | 27 | 0 | 7 | 0
Weight gain | 13 | 0 | 9 | 0
Neuropathy sensory | 26 | 0 | 10 | 0
Neuro-cortical | 5 | 1 | 6 | 1
Neuropathy motor | 4 | 0 | 2 | 0
Neuro-cerebellar | 2 | 0 | 2 | 0
Syncope | 2 | 1 | 1 | 0
Alopecia | 98 | N/A | 97 | N/A
Skin toxicity | 27 | 1 | 18 | 0
Nail disorders | 19 | 0 | 14 | 0
Nausea | 81 | 5 | 88 | 10
Stomatitis | 69 | 7 | 53 | 2
Vomiting | 45 | 4 | 59 | 7
Diarrhea | 35 | 4 | 28 | 2
Constipation | 34 | 1 | 32 | 1
Taste perversion | 28 | 1 | 15 | 0
Anorexia | 22 | 2 | 18 | 1
Abdominal Pain | 11 | 1 | 5 | 0
Amenorrhea | 62 | N/A | 52 | N/A
Cough | 14 | 0 | 10 | 0
Cardiac dysrhythmias | 8 | 0 | 6 | 0
Vasodilatation | 27 | 1 | 21 | 1
Hypotension | 2 | 0 | 1 | 0
Phlebitis | 1 | 0 | 1 | 0
Asthenia | 81 | 11 | 71 | 6
Myalgia | 27 | 1 | 10 | 0
Arthralgia | 19 | 1 | 9 | 0
Lacrimation disorder | 11 | 0 | 7 | 0
Conjunctivitis | 5 | 0 | 7 | 0
* COSTART term and grading system for events related to treatment.

Of the 744 patients treated with TAC, 36.3% experienced severe treatment-emergent adverse reactions compared to 26.6% of the 736 patients treated with FAC. Dose reductions due to hematologic toxicity occurred in 1% of cycles in the TAC arm versus 0.1% of cycles in the FAC arm. Six percent of patients treated with TAC discontinued treatment due to adverse reactions, compared to 1.1% treated with FAC; fever in the absence of infection and allergy being the most common reasons for withdrawal among TAC-treated patients. Two patients died in each arm within 30 days of their last study treatment; 1 death per arm was attributed to study drugs.

Fever and Infection

During the treatment period, fever in the absence of infection was seen in 46.5% of TAC-treated patients and in 17.1% of FAC-treated patients. Grade 3/4 fever in the absence of infection was seen in 1.3% and 0% of TAC- and FAC-treated patients, respectively. Infection was seen in 39.4% of TAC-treated patients compared to 36.3% of FAC-treated patients. Grade 3/4 infection was seen in 3.9% and 2.2% of TAC-treated and FAC-treated patients, respectively. There were no septic deaths in either treatment arm during the treatment period.

Gastrointestinal Reactions

In addition to gastrointestinal reactions reflected in the table above, 7 patients in the TAC arm were reported to have colitis/enteritis/large intestine perforation versus one patient in the FAC arm. Five of the 7 TAC-treated patients required treatment discontinuation; no deaths due to these events occurred during the treatment period.

Cardiovascular Reactions

More cardiovascular reactions were reported in the TAC arm versus the FAC arm during the treatment period: arrhythmias, all grades (6.2% vs 4.9%), and hypotension, all grades (1.9% vs 0.8%). Twenty-six (26) patients (3.5%) in the TAC arm and 17 patients (2.3%) in the FAC arm developed CHF during the study period. All except one patient in each arm were diagnosed with CHF during the follow-up period. Two (2) patients in TAC arm and 4 patients in FAC arm died due to CHF. The risk of CHF was higher in the TAC arm in the first year, and then was similar in both treatment arms.

Adverse reactions during the follow-up period (median follow-up time of 8 years)

In study TAX316, the most common adverse reactions that started during the treatment period and persisted into the follow-up period in TAC and FAC patients are described below (median follow-up time of 8 years).

Nervous system disorders

In study TAX316, peripheral sensory neuropathy started during the treatment period and persisted into the follow-up period in 84 patients (11.3%) in TAC arm and 15 patients (2%) in FAC arm. At the end of the follow-up period (median follow-up time of 8 years), peripheral sensory neuropathy was observed to be ongoing in 10 patients (1.3%) in TAC arm, and in 2 patients (0.3%) in FAC arm.

Skin and subcutaneous tissue disorders

In study TAX316, alopecia persisting into the follow-up period after the end of chemotherapy was reported in 687 of 744 TAC patients (92.3%) and 645 of 736 FAC patients (87.6%). At the end of the follow-up period (actual median follow-up time of 8 years), alopecia was observed to be ongoing in 29 TAC patients (3.9%) and 16 FAC patients (2.2%).

Reproductive system and breast disorders

In study TAX316, amenorrhea that started during the treatment period and persisted into the follow-up period after the end of chemotherapy was reported in 202 of 744 TAC patients (27.2%) and 125 of 736 FAC patients (17.0%). Amenorrhea was observed to be ongoing at the end of the follow-up period (median follow-up time of 8 years) in 121 of 744 TAC patients (16.3%) and 86 FAC patients (11.7%).

General disorders and administration site conditions

In study TAX316, peripheral edema that started during the treatment period and persisted into the follow-up period after the end of chemotherapy was observed in 119 of 744 TAC patients (16.0%) and 23 of 736 FAC patients (3.1%). At the end of the follow-up period (actual median follow-up time of 8 years), peripheral edema was ongoing in 19 TAC patients (2.6%) and 4 FAC patients (0.5%).

In study TAX316, lymphedema that started during the treatment period and persisted into the follow-up period after the end of chemotherapy was reported in 11 of 744 TAC patients (1.5%) and 1 of 736 FAC patients (0.1%). At the end of the follow-up period (actual median follow-up time of 8 years), lymphedema was observed to be ongoing in 6 TAC patients (0.8%) and 1 FAC patient (0.1%).

In study TAX316, asthenia that started during the treatment period and persisted into the follow-up period after the end of chemotherapy was reported in 236 of 744 TAC patients (31.7%) and 180 of 736 FAC patients (24.5%). At the end of the follow-up period (actual median follow-up time of 8 years), asthenia was observed to be ongoing in 29 TAC patients (3.9%) and 16 FAC patients (2.2%).

Acute myeloid leukemia (AML)/Myelodysplastic syndrome (MDS)

AML occurred in the adjuvant breast cancer trial (TAX316). The cumulative risk of developing treatment-related AML at median follow-up time of 8 years in TAX316 was 0.4% for TAC-treated patients and 0.1% for FAC-treated patients. One TAC patient (0.1%) and 1 FAC patient (0.1%) died due to AML during the follow-up period (median follow-up time of 8 years). Myelodysplastic syndrome occurred in 2 of 744 (0.3%) patients who received TAC and in 1 of 736 (0.1%) patients who received FAC. AML occurs at a higher frequency when these agents are given in combination with radiation therapy.

Lung Cancer

Monotherapy with Docetaxel Injection for unresectable, locally advanced or metastatic NSCLC previously treated with platinum-based chemotherapy

Docetaxel Injection 75 mg/m^2: Treatment-emergent adverse drug reactions are shown in Table 7. Included in this table are safety data for a total of 176 patients with non-small cell lung carcinoma and a history of prior treatment with platinum-based chemotherapy who were treated in two randomized, controlled trials. These reactions were described using NCI Common Toxicity Criteria regardless of relationship to study treatment, except for the hematologic toxicities or where otherwise noted.

Table 7 – Treatment-Emergent Adverse Reactions Regardless of Relationship to Treatment in Patients Receiving Docetaxel Injection as Monotherapy for Non-Small Cell Lung Cancer Previously Treated with Platinum-Based Chemotherapy*
 | Docetaxel Injection |  | Vinorelbine/
 | 75 mg/m^2 | Best Supportive Care | Ifosfamide
 | n=176 | n=49 | n=119
Adverse Reaction | % | % | %
Neutropenia
Any | 84 | 14 | 83
Grade 3/4 | 65 | 12 | 57
Leukopenia
Any | 84 | 6 | 89
Grade 3/4 | 49 | 0 | 43
Thrombocytopenia
Any | 8 | 0 | 8
Grade 3/4 | 3 | 0 | 2
Anemia
Any | 91 | 55 | 91
Grade 3/4 | 9 | 12 | 14
Febrile
Neutropenia** | 6 | NA† | 1
Infection
Any | 34 | 29 | 30
Grade 3/4 | 10 | 6 | 9
Treatment Related Mortality | 3 | NA† | 3
Hypersensitivity Reactions
Any | 6 | 0 | 1
Grade 3/4 | 3 | 0 | 0
Fluid Retention
Any | 34 | ND†† | 23
Severe | 3 |  | 3
Neurosensory
Any | 23 | 14 | 29
Grade 3/4 | 2 | 6 | 5
Neuromotor
Any | 16 | 8 | 10
Grade 3/4 | 5 | 6 | 3
Skin
Any | 20 | 6 | 17
Grade 3/4 | 1 | 2 | 1
Gastrointestinal
Nausea
Any | 34 | 31 | 31
Grade 3/4 | 5 | 4 | 8
Vomiting
Any | 22 | 27 | 22
Grade 3/4 | 3 | 2 | 6
Diarrhea
Any | 23 | 6 | 12
Grade 3/4 | 3 | 0 | 4
Alopecia | 56 | 35 | 50
Asthenia
Any | 53 | 57 | 54
Severe*** | 18 | 39 | 23
Stomatitis
Any | 26 | 6 | 8
Grade 3/4 | 2 | 0 | 1
Pulmonary
Any | 41 | 49 | 45
Grade 3/4 | 21 | 29 | 19
Nail Disorder
Any | 11 | 0 | 2
Severe*** | 1 | 0 | 0
Myalgia
Any | 6 | 0 | 3
Severe*** | 0 | 0 | 0
Arthralgia
Any | 3 | 2 | 2
Severe*** | 0 | 0 | 1
Taste Perversion
Any | 6 | 0 | 0
Severe*** | 1 | 0 | 0
*Normal Baseline LFTs: Transaminases ≤1.5 times ULN or alkaline phosphatase ≤2.5 times ULN or isolated elevations of transaminases or alkaline phosphatase up to 5 times ULN
**Febrile Neutropenia: ANC grade 4 with fever >38°C with intravenous antibiotics and/or hospitalization
***COSTART term and grading system
†Not Applicable
†† Not Done

Combination therapy with Docetaxel Injection in chemotherapy-naive advanced unresectable or metastatic NSCLC

Table 8 presents safety data from two arms of an open label, randomized controlled trial (TAX326) that enrolled patients with unresectable stage IIIB or IV non-small cell lung cancer and no history of prior chemotherapy. Adverse reactions were described using the NCI Common Toxicity Criteria except where otherwise noted.

Table 8 - Adverse Reactions Regardless of Relationship to Treatment in Chemotherapy-Naive Advanced Non-Small Cell Lung Cancer Patients Receiving Docetaxel Injection in Combination with Cisplatin
 | Docetaxel Injection 75 mg/m^2 | Vinorelbine 25 mg/m^2 +
 | + Cisplatin | Cisplatin
 | 75 mg/m^2 | 100 mg/m^2
Adverse Reaction | n=406 | n=396
 | % | %
Neutropenia
Any | 91 | 90
Grade 3/4 | 74 | 78
Febrile Neutropenia | 5 | 5
Thrombocytopenia
Any | 15 | 15
Grade 3/4 | 3 | 4
Anemia
Any | 89 | 94
Grade 3/4 | 7 | 25
Infection
Any | 35 | 37
Grade 3/4 | 8 | 8
Fever in absence of infection
Any | 33 | 29
Grade 3/4 | < 1 | 1
Hypersensitivity Reaction*
Any | 12 | 4
Grade 3/4 | 3 | < 1
Fluid Retention**
Any | 54 | 42
All severe or life-threatening events | 2 | 2
Pleural effusion
Any | 23 | 22
All severe or life-threatening events | 2 | 2
Peripheral edema
Any | 34 | 18
All severe or life-threatening events | <1 | <1
Weight gain
Any | 15 | 9
All severe or life-threatening events | <1 | <1
Neurosensory
Any | 47 | 42
Grade 3/4 | 4 | 4
Neuromotor
Any | 19 | 17
Grade 3/4 | 3 | 6
Skin
Any | 16 | 14
Grade 3/4 | <1 | 1
Nausea
Any | 72 | 76
Grade 3/4 | 10 | 17
Vomiting
Any | 55 | 61
Grade 3/4 | 8 | 16
Diarrhea
Any | 47 | 25
Grade 3/4 | 7 | 3
Anorexia**
Any | 42 | 40
All severe or life-threatening events | 5 | 5
Stomatitis
Any | 24 | 21
Grade 3/4 | 2 | 1
Alopecia
Any | 75 | 42
Grade 3 | <1 | 0
Asthenia**
Any | 74 | 75
All severe or life-threatening events | 12 | 14
Nail Disorder**
Any | 14 | <1
All severe events | <1 | 0
Myalgia**
Any | 18 | 12
All severe events | <1 | <1
* Replaces NCI term “Allergy”
** COSTART term and grading system

Deaths within 30 days of last study treatment occurred in 31 patients (7.6%) in the docetaxel+cisplatin arm and 37 patients (9.3%) in the vinorelbine+cisplatin arm. Deaths within 30 days of last study treatment attributed to study drug occurred in 9 patients (2.2%) in the docetaxel+cisplatin arm and 8 patients (2.0%) in the vinorelbine+cisplatin arm.

The second comparison in the study, vinorelbine+cisplatin versus Docetaxel Injection+carboplatin (which did not demonstrate a superior survival associated with Docetaxel Injection [see Clinical Studies (14.3)]) demonstrated a higher incidence of thrombocytopenia, diarrhea, fluid retention, hypersensitivity reactions, skin toxicity, alopecia and nail changes on the Docetaxel Injection+carboplatin arm, while a higher incidence of anemia, neurosensory toxicity, nausea, vomiting, anorexia and asthenia was observed on the vinorelbine+cisplatin arm.

Prostate Cancer

Combination therapy with Docetaxel Injection in patients with prostate cancer

The following data are based on the experience of 332 patients, who were treated with Docetaxel Injection 75 mg/m^2 every 3 weeks in combination with prednisone 5 mg orally twice daily (see Table 9).

Table 9 - Clinically Important Treatment-Emergent Adverse Reactions (Regardless of Relationship) in Patients with Prostate Cancer who Received Docetaxel Injection in Combination with Prednisone (TAX327)
 | Docetaxel Injection 75 mg/m^2 |  | Mitoxantrone 12 mg/m^2
 | every 3 weeks + |  | every 3 weeks +
 | prednisone 5 mg twice daily |  | prednisone 5 mg twice daily
 | n=332 |  | n=335
 | % |  | %
Adverse Reaction | Any | Grade 3/4 | Any | Grade 3/4
Anemia | 67 | 5 | 58 | 2
Neutropenia | 41 | 32 | 48 | 22
Thrombocytopenia | 3 | 1 | 8 | 1
Febrile neutropenia | 3 | N/A | 2 | N/A
Infection | 32 | 6 | 20 | 4
Epistaxis | 6 | 0 | 2 | 0
Allergic Reactions | 8 | 1 | 1 | 0
Fluid Retention* | 24 | 1 | 5 | 0
Weight Gain* | 8 | 0 | 3 | 0
Peripheral Edema* | 18 | 0 | 2 | 0
Neuropathy Sensory | 30 | 2 | 7 | 0
Neuropathy Motor | 7 | 2 | 3 | 1
Rash/Desquamation | 6 | 0 | 3 | 1
Alopecia | 65 | N/A | 13 | N/A
Nail Changes | 30 | 0 | 8 | 0
Nausea | 41 | 3 | 36 | 2
Diarrhea | 32 | 2 | 10 | 1
Stomatitis/Pharyngitis | 20 | 1 | 8 | 0
Taste Disturbance | 18 | 0 | 7 | 0
Vomiting | 17 | 2 | 14 | 2
Anorexia | 17 | 1 | 14 | 0
Cough | 12 | 0 | 8 | 0
Dyspnea | 15 | 3 | 9 | 1
Cardiac left ventricular function | 10 | 0 | 22 | 1
Fatigue | 53 | 5 | 35 | 5
Myalgia | 15 | 0 | 13 | 1
Tearing | 10 | 1 | 2 | 0
Arthralgia | 8 | 1 | 5 | 1
*Related to treatment

Gastric Cancer

Combination therapy with Docetaxel Injection in gastric adenocarcinoma

Data in the following table are based on the experience of 221 patients with advanced gastric adenocarcinoma and no history of prior chemotherapy for advanced disease who were treated with Docetaxel Injection 75 mg/m^2 in combination with cisplatin and fluorouracil (see Table 10).

Table 10 - Clinically Important Treatment-Emergent Adverse Reactions Regardless of Relationship to Treatment in the Gastric Cancer Study
 | Docetaxel Injection 75 mg/m^2 +
 | cisplatin 75 mg/m^2 + |  | Cisplatin 100 mg/m^2 +
 | fluorouracil 750 mg/m^2 |  | fluorouracil 1000 mg/m^2
 | n=221 |  | n=224
Adverse Reaction | Any | Grade 3/4 | Any | Grade 3/4
 | % | % | % | %
Anemia | 97 | 18 | 93 | 26
Neutropenia | 96 | 82 | 83 | 57
Fever in the absence of infection | 36 | 2 | 23 | 1
Thrombocytopenia | 26 | 8 | 39 | 14
Infection | 29 | 16 | 23 | 10
Febrile neutropenia | 16 | N/A | 5 | N/A
Neutropenic infection | 16 | N/A | 10 | N/A
Allergic reactions | 10 | 2 | 6 | 0
Fluid retention* | 15 | 0 | 4 | 0
Edema* | 13 | 0 | 3 | 0
Lethargy | 63 | 21 | 58 | 18
Neurosensory | 38 | 8 | 25 | 3
Neuromotor | 9 | 3 | 8 | 3
Dizziness | 16 | 5 | 8 | 2
Alopecia | 67 | 5 | 41 | 1
Rash/itch | 12 | 1 | 9 | 0
Nail changes | 8 | 0 | 0 | 0
Skin desquamation | 2 | 0 | 0 | 0
Nausea | 73 | 16 | 76 | 19
Vomiting | 67 | 15 | 73 | 19
Anorexia | 51 | 13 | 54 | 12
Stomatitis | 59 | 21 | 61 | 27
Diarrhea | 78 | 20 | 50 | 8
Constipation | 25 | 2 | 34 | 3
Esophagitis/dysphagia/odynophagia | 16 | 2 | 14 | 5
Gastrointestinal pain/cramping | 11 | 2 | 7 | 3
Cardiac dysrhythmias | 5 | 2 | 2 | 1
Myocardial ischemia | 1 | 0 | 3 | 2
Tearing | 8 | 0 | 2 | 0
Altered hearing | 6 | 0 | 13 | 2
Clinically important treatment-emergent adverse reactions were determined based upon frequency, severity, and clinical impact of the adverse reaction.
*Related to treatment

Head and Neck Cancer

Combination therapy with Docetaxel Injection in head and neck cancer

Table 11 summarizes the safety data obtained from patients that received induction chemotherapy with Docetaxel Injection 75 mg/m^2 in combination with cisplatin and fluorouracil followed by radiotherapy (TAX323; 174 patients) or chemoradiotherapy (TAX324; 251 patients). The treatment regimens are described in Section 14.6.

Table 11 – Clinically Important Treatment-Emergent Adverse Reactions (Regardless of Relationship) in Patients with SCCHN Receiving Induction Chemotherapy with Docetaxel Injection in Combination with Cisplatin and Fluorouracil Followed by Radiotherapy (TAX323) or Chemoradiotherapy (TAX324)
 | TAX323 |  |  |  | TAX324
 | (n=355) |  |  |  | (n=494)
 | Docetaxel Injection arm |  | Comparator arm |  | Docetaxel Injection arm |  | Comparator arm
 | (n=174) |  | (n=181) |  | (n=251) |  | (n=243)
 | Any | Grade | Any | Grade | Any | Grade | Any | Grade
Adverse Reaction | % | 3/4 | % | 3/4 | % | 3/4 | % | 3/4
(by Body System) |  | % |  | % |  | % |  | %
Neutropenia | 93 | 76 | 87 | 53 | 95 | 84 | 84 | 56
Anemia | 89 | 9 | 88 | 14 | 90 | 12 | 86 | 10
Thrombocytopenia | 24 | 5 | 47 | 18 | 28 | 4 | 31 | 11
Infection | 27 | 9 | 26 | 8 | 23 | 6 | 28 | 5
Febrile neutropenia* | 5 | N/A | 2 | N/A | 12 | N/A | 7 | N/A
Neutropenic infection | 14 | N/A | 8 | N/A | 12 | N/A | 8 | N/A
Cancer pain | 21 | 5 | 16 | 3 | 17 | 9 | 20 | 11
Lethargy | 41 | 3 | 38 | 3 | 61 | 5 | 56 | 10
Fever in the absence of infection | 32 | 1 | 37 | 0 | 30 | 4 | 28 | 3
Myalgia | 10 | 1 | 7 | 0 | 7 | 0 | 7 | 2
Weight loss | 21 | 1 | 27 | 1 | 14 | 2 | 14 | 2
Allergy | 6 | 0 | 3 | 0 | 2 | 0 | 0 | 0
Fluid retention** | 20 | 0 | 14 | 1 | 13 | 1 | 7 | 2
Edema only | 13 | 0 | 7 | 0 | 12 | 1 | 6 | 1
Weight gain only | 6 | 0 | 6 | 0 | 0 | 0 | 1 | 0
Dizziness | 2 | 0 | 5 | 1 | 16 | 4 | 15 | 2
Neurosensory | 18 | 1 | 11 | 1 | 14 | 1 | 14 | 0
Altered hearing | 6 | 0 | 10 | 3 | 13 | 1 | 19 | 3
Neuromotor | 2 | 1 | 4 | 1 | 9 | 0 | 10 | 2
Alopecia | 81 | 11 | 43 | 0 | 68 | 4 | 44 | 1
Rash/itch | 12 | 0 | 6 | 0 | 20 | 0 | 16 | 1
Dry skin | 6 | 0 | 2 | 0 | 5 | 0 | 3 | 0
Desquamation | 4 | 1 | 6 | 0 | 2 | 0 | 5 | 0
Nausea | 47 | 1 | 51 | 7 | 77 | 14 | 80 | 14
Stomatitis | 43 | 4 | 47 | 11 | 66 | 21 | 68 | 27
Vomiting | 26 | 1 | 39 | 5 | 56 | 8 | 63 | 10
Diarrhea | 33 | 3 | 24 | 4 | 48 | 7 | 40 | 3
Constipation | 17 | 1 | 16 | 1 | 27 | 1 | 38 | 1
Anorexia | 16 | 1 | 25 | 3 | 40 | 12 | 34 | 12
Esophagitis/dysphagia/ Odynophagia | 13 | 1 | 18 | 3 | 25 | 13 | 26 | 10
Taste, sense of smell altered | 10 | 0 | 5 | 0 | 20 | 0 | 17 | 1
Gastrointestinal pain/cramping | 8 | 1 | 9 | 1 | 15 | 5 | 10 | 2
Heartburn | 6 | 0 | 6 | 0 | 13 | 2 | 13 | 1
Gastrointestinal bleeding | 4 | 2 | 0 | 0 | 5 | 1 | 2 | 1
Cardiac dysrhythmia | 2 | 2 | 2 | 1 | 6 | 3 | 5 | 3
Venous*** | 3 | 2 | 6 | 2 | 4 | 2 | 5 | 4
Ischemia myocardial | 2 | 2 | 1 | 0 | 2 | 1 | 1 | 1
Tearing | 2 | 0 | 1 | 0 | 2 | 0 | 2 | 0
Conjunctivitis | 1 | 0 | 1 | 0 | 1 | 0 | 0.4 | 0
Clinically important treatment-emergent adverse reactions based upon frequency, severity, and clinical impact.
*Febrile neutropenia: grade ≥2 fever concomitant with grade 4 neutropenia requiring intravenous antibiotics and/or
hospitalization.
**Related to treatment.
*** Includes superficial and deep vein thrombosis and pulmonary embolism

6.2 Postmarketing Experience

The following adverse reactions have been identified from clinical trials and/or postmarketing surveillance. Because these reactions are reported from a population of uncertain size, it is not always possible to reliably estimate their frequency or establish a causal relationship to drug exposure.

Body as a whole: diffuse pain, chest pain, radiation recall phenomenon, injection site recall reaction (recurrence of skin reaction at a site of previous extravasation following administration of docetaxel at a different site) at the site of previous extravasation.

Cardiovascular: atrial fibrillation, deep vein thrombosis, ECG abnormalities, thrombophlebitis, pulmonary embolism, syncope, tachycardia, myocardial infarction. Ventricular arrhythmia, including ventricular tachycardia, in patients treated with docetaxel in combination regimens including doxorubicin, 5-fluorouracil and/or cyclophosphamide may be associated with fatal outcome.

Cutaneous: cutaneous lupus erythematosus, bullous eruptions such as erythema multiforme and severe cutaneous adverse reactions (SCARs) such as Stevens-Johnson syndrome, toxic epidermal necrolysis and acute generalized exanthematous pustulosis, scleroderma-like changes (usually preceded by peripheral lymphedema), severe palmar-plantar erythrodysesthesia, and permanent alopecia.

Gastrointestinal: enterocolitis, including colitis, ischemic colitis, and neutropenic enterocolitis, which may be fatal. Abdominal pain, anorexia, constipation, duodenal ulcer, esophagitis, gastrointestinal hemorrhage, gastrointestinal perforation, intestinal obstruction, ileus, and dehydration as a consequence of gastrointestinal events.

Hearing: ototoxicity, hearing disorders and/or hearing loss, including during use with other ototoxic drugs.

Hematologic: bleeding episodes, disseminated intravascular coagulation (DIC), often in association with sepsis or multiorgan failure.

Hepatic: hepatitis, sometimes fatal, primarily in patients with pre-existing liver disorders.

Hypersensitivity: anaphylactic shock with fatal outcome in patients who received premedication. Severe hypersensitivity reactions with fatal outcome with docetaxel in patients who previously experienced hypersensitivity reactions to paclitaxel.

Metabolism and nutrition disorders: electrolyte imbalance, including hyponatremia, hypokalemia, hypomagnesemia, and hypocalcemia. Tumor lysis syndrome, sometimes fatal.

Neurologic: confusion, seizures or transient loss of consciousness, sometimes appearing during the infusion of the drug.

Ophthalmologic: conjunctivitis, lacrimation or lacrimation with or without conjunctivitis, cystoid macular edema (CME). Excessive tearing which may be attributable to lacrimal duct obstruction. Transient visual disturbances (flashes, flashing lights, scotomata), typically occurring during drug infusion and reversible upon discontinuation of the infusion, in association with hypersensitivity reactions.

Respiratory: dyspnea, acute pulmonary edema, acute respiratory distress syndrome/pneumonitis, interstitial lung disease, interstitial pneumonia, respiratory failure, and pulmonary fibrosis, which may be fatal. Radiation pneumonitis in patients receiving concomitant radiotherapy.

Renal: renal insufficiency and renal failure, the majority of cases were associated with concomitant nephrotoxic drugs.

Second primary malignancies: second primary malignancies, including AML, MDS, NHL, and renal cancer [see Warnings and Precautions (5.7)].

Musculoskeletal disorder: myositis.

7 DRUG INTERACTIONS

Docetaxel is a CYP3A4 substrate. In vitro studies have shown that the metabolism of docetaxel may be modified by the concomitant administration of compounds that induce, inhibit, or are metabolized by cytochrome P450 3A4.

In vivo studies showed that the exposure of docetaxel increased 2.2-fold when it was coadministered with ketoconazole, a potent inhibitor of CYP3A4. Protease inhibitors, particularly ritonavir, may increase the exposure of docetaxel. Concomitant use of Docetaxel Injection and drugs that inhibit CYP3A4 may increase exposure to docetaxel and should be avoided. In patients receiving treatment with Docetaxel Injection, close monitoring for toxicity and a Docetaxel Injection dose reduction could be considered if systemic administration of a potent CYP3A4 inhibitor cannot be avoided [see Dosage and Administration (2.7), Clinical Pharmacology (12.3)].

8 USE IN SPECIFIC POPULATIONS

8.1 Pregnancy

Risk Summary

Based on findings in animal reproduction studies and its mechanism of action, Docetaxel Injection can cause fetal harm when administered to a pregnant woman [see Clinical Pharmacology (12.1)]. Available data from case reports in the literature and pharmacovigilance with docetaxel use in pregnant women are not sufficient to inform the drug-associated risk of major birth defects, miscarriage, or adverse maternal or fetal outcomes. Docetaxel Injection contains alcohol which can interfere with neurobehavioral development [see Clinical Considerations]. In animal reproductive studies, administration of docetaxel to pregnant rats and rabbits during the period of organogenesis caused an increased incidence of embryo-fetal toxicities, including intrauterine mortality, at doses as low as 0.02 and 0.003 times the recommended human dose based on body surface area, respectively [see Data]. Advise pregnant women and females of reproductive potential of the potential risk to a fetus.

The estimated background risk of major birth defects and miscarriage for the indicated populations is unknown. All pregnancies have a background risk of birth defect, miscarriage, or other adverse outcomes. In the U.S. general population, the estimated background risk of major birth defects and miscarriage in clinically recognized pregnancies is 2% to 4% and 15% to 20%, respectively.

Clinical Considerations

Docetaxel Injection contains alcohol [see Warnings and Precautions (5.13)]. Published studies have demonstrated that alcohol is associated with fetal harm including central nervous system abnormalities, behavioral disorders, and impaired intellectual development.

Data

Animal data

Intravenous administration of ≥0.3 and 0.03 mg/kg/day docetaxel to pregnant rats and rabbits, respectively, during the period of organogenesis caused an increased incidence of intrauterine mortality, resorptions, reduced fetal weights, and fetal ossification delays. Maternal toxicity was also observed at these doses, which were approximately 0.02 and 0.003 times the daily maximum recommended human dose based on body surface area, respectively.

8.2 Lactation

Risk Summary

There is no information regarding the presence of docetaxel in human milk, or on its effects on milk production or the breastfed child. No lactation studies in animals have been conducted. Because of the potential for serious adverse reactions in a breastfed child, advise women not to breastfeed during treatment with Docetaxel Injection and for 1 week after the last dose.

8.3 Females and Males of Reproductive Potential

Based on findings in animals, Docetaxel Injection can cause fetal harm when administered to a pregnant woman [see Use in Specific Populations (8.1)].

Pregnancy Testing

Verify pregnancy status in females of reproductive potential prior to initiating Docetaxel Injection.

Contraception

Females

Based on genetic toxicity findings, advise females of reproductive potential to use effective contraception during treatment and for 2 months after the last dose of Docetaxel Injection.

Males

Based on genetic toxicity findings, advise male patients with female partners of reproductive potential to use effective contraception during treatment and for 4 months after the last dose of Docetaxel Injection.

Infertility

Based on findings in animal studies, Docetaxel Injection may impair fertility in males of reproductive potential [see Nonclinical Toxicology (13.1)].

8.4 Pediatric Use

The alcohol content of Docetaxel Injection should be taken into account when given to pediatric patients [see Warnings and Precautions (5.13)].

The efficacy of docetaxel in pediatric patients as monotherapy or in combination has not been established. The overall safety profile of docetaxel in pediatric patients receiving monotherapy or TCF was consistent with the known safety profile in adults.

Docetaxel has been studied in a total of 289 pediatric patients: 239 in 2 trials with monotherapy and 50 in combination treatment with cisplatin and 5-fluorouracil (TCF).

Docetaxel Monotherapy

Docetaxel monotherapy was evaluated in a dose-finding phase 1 trial in 61 pediatric patients (median age 12.5 years, range 1 to 22 years) with a variety of refractory solid tumors. The recommended dose was 125 mg/m^2 as a 1-hour intravenous infusion every 21 days. The primary dose limiting toxicity was neutropenia.

The recommended dose for docetaxel monotherapy was evaluated in a phase 2 single-arm trial in 178 pediatric patients (median age 12 years, range 1 to 26 years) with a variety of recurrent/refractory solid tumors. Efficacy was not established with tumor response rates ranging from one complete response (CR) (0.6%) in a patient with undifferentiated sarcoma to four partial responses (2.2%) seen in one patient each with Ewing Sarcoma, neuroblastoma, osteosarcoma, and squamous cell carcinoma.

Docetaxel in Combination

Docetaxel was studied in combination with cisplatin and 5-fluorouracil (TCF) versus cisplatin and 5-fluorouracil (CF) for the induction treatment of nasopharyngeal carcinoma (NPC) in pediatric patients prior to chemoradiation consolidation. Seventy-five patients (median age 16 years, range 9 to 21 years) were randomized (2:1) to docetaxel (75 mg/m^2) in combination with cisplatin (75 mg/m^2) and 5-fluorouracil (750 mg/m^2) (TCF) or to cisplatin (80 mg/m^2) and 5-fluorouracil (1000 mg/m^2/day) (CF). The primary endpoint was the CR rate following induction treatment of NPC. One patient out of 50 in the TCF group (2%) had a complete response while none of the 25 patients in the CF group had a complete response.

Pharmacokinetics

Pharmacokinetic parameters for docetaxel were determined in 2 pediatric solid tumor trials. Following docetaxel administration at 55 mg/m^2 to 235 mg/m^2 in a 1-hour intravenous infusion every 3 weeks in 25 patients aged 1 to 20 years (median 11 years), docetaxel clearance was 17.3±10.9 L/h/m^2.

Docetaxel was administered in combination with cisplatin and 5-fluorouracil (TCF), at dose levels of 75 mg/m^2 in a 1-hour intravenous infusion day 1 in 28 patients aged 10 to 21 years (median 16 years, 17 patients were older than 16). Docetaxel clearance was 17.9±8.75 L/h/m^2, corresponding to an AUC of 4.20±2.57 mcg•h/mL.

In summary, the body surface area adjusted clearance of docetaxel monotherapy and TCF combination in children were comparable to those in adults [see Clinical Pharmacology (12.3)].

8.5 Geriatric Use

In general, dose selection for an elderly patient should be cautious, reflecting the greater frequency of decreased hepatic, renal, or cardiac function and of concomitant disease or other drug therapy in elderly patients.

Non-Small Cell Lung Cancer

In a study conducted in chemotherapy-naive patients with NSCLC (TAX326), 148 patients (36%) in the Docetaxel Injection+cisplatin group were 65 years of age or greater. There were 128 patients (32%) in the vinorelbine+cisplatin group 65 years of age or greater. In the Docetaxel Injection+cisplatin group, patients less than 65 years of age had a median survival of 10.3 months (95% CI: 9.1 months, 11.8 months) and patients 65 years or older had a median survival of 12.1 months (95% CI: 9.3 months, 14 months). In patients 65 years of age or greater treated with Docetaxel Injection+cisplatin, diarrhea (55%), peripheral edema (39%) and stomatitis (28%) were observed more frequently than in the vinorelbine+cisplatin group (diarrhea 24%, peripheral edema 20%, stomatitis 20%). Patients treated with Docetaxel Injection+cisplatin who were 65 years of age or greater were more likely to experience diarrhea (55%), infections (42%), peripheral edema (39%) and stomatitis (28%) compared to patients less than the age of 65 administered the same treatment (43%, 31%, 31% and 21%, respectively).

When Docetaxel Injection was combined with carboplatin for the treatment of chemotherapy-naive, advanced non-small cell lung carcinoma, patients 65 years of age or greater (28%) experienced higher frequency of infection compared to similar patients treated with Docetaxel Injection+cisplatin, and a higher frequency of diarrhea, infection and peripheral edema than elderly patients treated with vinorelbine+cisplatin.

Prostate Cancer

Of the 333 patients treated with Docetaxel Injection every three weeks plus prednisone in the prostate cancer study (TAX327), 209 patients were 65 years of age or greater and 68 patients were older than 75 years. In patients treated with Docetaxel Injection every three weeks, the following treatment-emergent adverse reactions occurred at rates ≥10% higher in patients 65 years of age or greater compared to younger patients: anemia (71% vs. 59%), infection (37% vs. 24%), nail changes (34% vs. 23%), anorexia (21% vs. 10%), weight loss (15% vs. 5%) respectively.

Breast Cancer

In the adjuvant breast cancer trial (TAX316), Docetaxel Injection in combination with doxorubicin and cyclophosphamide was administered to 744 patients of whom 48 (6%) were 65 years of age or greater. The number of elderly patients who received this regimen was not sufficient to determine whether there were differences in safety and efficacy between elderly and younger patients.

Gastric Cancer

Among the 221 patients treated with Docetaxel Injection in combination with cisplatin and fluorouracil in the gastric cancer study, 54 were 65 years of age or older and 2 patients were older than 75 years. In this study, the number of patients who were 65 years of age or older was insufficient to determine whether they respond differently from younger patients. However, the incidence of serious adverse reactions was higher in the elderly patients compared to younger patients. The incidence of the following adverse reactions (all grades, regardless of relationship): lethargy, stomatitis, diarrhea, dizziness, edema, febrile neutropenia/neutropenic infection occurred at rates ≥10% higher in patients who were 65 years of age or older compared to younger patients. Elderly patients treated with TCF should be closely monitored.

Head and Neck Cancer

Among the 174 and 251 patients who received the induction treatment with Docetaxel Injection in combination with cisplatin and fluorouracil (TPF) for SCCHN in the TAX323 and TAX324 studies, 18 (10%) and 32 (13%) of the patients were 65 years of age or older, respectively.

These clinical studies of Docetaxel Injection in combination with cisplatin and fluorouracil in patients with SCCHN did not include sufficient numbers of patients aged 65 and over to determine whether they respond differently from younger patients. Other reported clinical experience with this treatment regimen has not identified differences in responses between elderly and younger patients.

8.6 Hepatic Impairment

Avoid Docetaxel Injection in patients with bilirubin >ULN and patients with AST and/or ALT >1.5 x ULN concomitant with alkaline phosphatase >2.5 x ULN [see Boxed Warning, Warnings and Precautions (5.2), Clinical Pharmacology (12.3)].

The alcohol content of Docetaxel Injection should be taken into account when given to patients with hepatic impairment [see Warnings and Precautions (5.13)].

10 OVERDOSAGE

There is no known antidote for Docetaxel Injection overdosage. In case of overdosage, the patient should be kept in a specialized unit where vital functions can be closely monitored. Anticipated complications of overdosage include: bone marrow suppression, peripheral neurotoxicity, and mucositis. Patients should receive therapeutic G-CSF as soon as possible after discovery of overdose. Other appropriate symptomatic measures should be taken, as needed.

In two reports of overdose, one patient received 150 mg/m^2 and the other received 200 mg/m^2 as 1-hour infusions. Both patients experienced severe neutropenia, mild asthenia, cutaneous reactions, and mild paresthesia, and recovered without incident.

In mice, lethality was observed following single intravenous doses that were ≥154 mg/kg (about 4.5 times the human dose of 100 mg/m^2 on a mg/m^2 basis); neurotoxicity associated with paralysis, non-extension of hind limbs, and myelin degeneration was observed in mice at 48 mg/kg (about 1.5 times the human dose of 100 mg/m^2 basis). In male and female rats, lethality was observed at a dose of 20 mg/kg (comparable to the human dose of 100 mg/m^2 on a mg/m^2 basis) and was associated with abnormal mitosis and necrosis of multiple organs.

11 DESCRIPTION

Docetaxel, USP is an antineoplastic agent belonging to the taxoid family. It is prepared by semisynthesis beginning with a precursor extracted from the renewable needle biomass of yew plants. The chemical name for docetaxel, USP is (2R,3S)-N-carboxy-3-phenylisoserine,N-tert-butyl ester, 13-ester with 5β-20-epoxy-1,2α,4,7β,10β,13α-hexahydroxytax-11-en-9-one 4-acetate 2-benzoate, anhydrous. Docetaxel, USP has the following structural formula:

Docetaxel, USP is a white to almost-white powder with an empirical formula of C43H53NO14, and a molecular weight of 807.88. It is highly lipophilic and practically insoluble in water.

One-vial Docetaxel Injection, USP

Docetaxel Injection, USP is a sterile, non-pyrogenic, clear, viscous, colorless to pale yellow solution, without macroscopic particles in solution at 20 mg/mL docetaxel concentration.

Each mL contains 20 mg docetaxel, USP, citric acid anhydrous (6 mg), kollidon 12 PF (povidone P12) (100 mg), polysorbate 80 (424 mg) and ethanol (400 mg, 50% v/v).

Docetaxel Injection, USP is available in single-dose vials containing 20 mg (1 mL) or 80 mg (4 mL), docetaxel.

Docetaxel Injection, USP requires NO prior dilution with a diluent and is ready to add to the infusion solution.

12 CLINICAL PHARMACOLOGY

12.1 Mechanism of Action

Docetaxel is an antineoplastic agent that acts by disrupting the microtubular network in cells that is essential for mitotic and interphase cellular functions. Docetaxel binds to free tubulin and promotes the assembly of tubulin into stable microtubules while simultaneously inhibiting their disassembly. This leads to the production of microtubule bundles without normal function and to the stabilization of microtubules, which results in the inhibition of mitosis in cells. Docetaxel’s binding to microtubules does not alter the number of protofilaments in the bound microtubules, a feature which differs from most spindle poisons currently in clinical use.

12.3 Pharmacokinetics

Absorption

The pharmacokinetics of docetaxel has been evaluated in cancer patients after administration of 20 mg/m^2 to 115 mg/m^2 in phase 1 studies. The area under the curve (AUC) was dose proportional following doses of 70 mg/m^2 to 115 mg/m^2 with infusion times of 1 to 2 hours. Docetaxel’s pharmacokinetic profile is consistent with a three-compartment pharmacokinetic model, with initial rapid distribution phase and the late (terminal) phase.

Distribution

Mean steady state volume of distribution was 113 L. Docetaxel is approximately 94% protein bound in vitro, mainly to α1-acid glycoprotein, albumin, and lipoproteins. In three cancer patients, the in vitro binding to plasma proteins was approximately 97%. Dexamethasone does not affect the protein binding of docetaxel.

Elimination

With extended plasma sampling up to 8 to 22 days post infusion, the estimated mean total body clearance was 18 L/h/m^2 (range of means: 14 to 23) and mean terminal elimination half-life was 116 hours (range of means: 92 to 135).

Metabolism

Docetaxel is metabolized by the CYP3A4 isoenzyme in vitro [see Drug Interactions (7)].

Excretion

In three cancer patients urinary and fecal excretion accounted for approximately 6% and 75% of the administered radioactivity, respectively, within 7 days. About 80% of the radioactivity recovered in feces was excreted during the first 48 hours as 1 major and 3 minor metabolites with less than 8% as unchanged drug.

Specific Populations

Effect of Age: A population pharmacokinetic analysis was carried out after docetaxel treatment of 535 patients dosed at 100 mg/m^2. Pharmacokinetic parameters estimated by this analysis were very close to those estimated from phase 1 studies. The pharmacokinetics of docetaxel was not influenced by age.

Effect of Gender: The population pharmacokinetics analysis described above also indicated that gender did not influence the pharmacokinetics of docetaxel.

Hepatic Impairment: The population pharmacokinetic analysis described above indicated that in patients with clinical chemistry data suggestive of mild to moderate liver impairment (AST and/or ALT >1.5 times ULN concomitant with alkaline phosphatase >2.5 times ULN), total body clearance was lowered by an average of 27%, resulting in a 38% increase in systemic exposure (AUC). This average, however, includes a substantial range and there is, at present, no measurement that would allow recommendation for dose adjustment in such patients. Patients with combined abnormalities of transaminase and alkaline phosphatase should not be treated with Docetaxel Injection. Patients with severe hepatic impairment have not been studied [see Warnings and Precautions (5.2), Use in Specific Populations (8.6)].

Effect of Race: Mean total body clearance for Japanese patients dosed at the range of 10 mg/m^2 to 90 mg/m^2 was similar to that of European/American populations dosed at 100 mg/m^2, suggesting no significant difference in the elimination of docetaxel in the two populations.

Drug Interaction Studies

Effect of Ketoconazole: The effect of ketoconazole (a strong CYP3A4 inhibitor) on the pharmacokinetics of docetaxel was investigated in 7 cancer patients. Patients were randomized to receive either docetaxel (100 mg/m^2 intravenous) alone or docetaxel (10 mg/m^2 intravenous) in combination with ketoconazole (200 mg orally once daily for 3 days) in a crossover design with a 3-week washout period. The results of this study indicated that the mean dose-normalized AUC of docetaxel was increased 2.2-fold and its clearance was reduced by 49% when docetaxel was co-administered with ketoconazole [see Dosage and Administration (2.7), Drug Interactions (7)].

Effect of Combination Therapies:

- Dexamethasone: Docetaxel total body clearance was not modified by pretreatment with dexamethasone.
- Cisplatin: Clearance of docetaxel in combination therapy with cisplatin was similar to that previously observed following monotherapy with docetaxel. The pharmacokinetic profile of cisplatin in combination therapy with docetaxel was similar to that observed with cisplatin alone.
- Cisplatin and Fluorouracil: The combined administration of docetaxel, cisplatin and fluorouracil in 12 patients with solid tumors had no influence on the pharmacokinetics of each individual drug.
- Prednisone: A population pharmacokinetic analysis of plasma data from 40 patients with metastatic castration-resistant prostate cancer indicated that docetaxel systemic clearance in combination with prednisone is similar to that observed following administration of docetaxel alone.
- Cyclophosphamide and Doxorubicin: A study was conducted in 30 patients with advanced breast cancer to determine the potential for drug-drug interactions between docetaxel (75 mg/m^2), doxorubicin (50 mg/m^2), and cyclophosphamide (500 mg/m^2) when administered in combination. The coadministration of docetaxel had no effect on the pharmacokinetics of doxorubicin and cyclophosphamide when the three drugs were given in combination compared to coadministration of doxorubicin and cyclophosphamide only. In addition, doxorubicin and cyclophosphamide had no effect on docetaxel plasma clearance when the three drugs were given in combination compared to historical data for docetaxel monotherapy.

13 NONCLINICAL TOXICOLOGY

13.1 Carcinogenesis, Mutagenesis, Impairment of Fertility

Carcinogenicity studies with docetaxel have not been performed.

Docetaxel was genotoxic by an aneugenic mechanism in the in vitro chromosome aberration test in CHO-K1 cells and in the in vivo micronucleus test in mice administered doses of 0.39 to 1.56 mg/kg (about 1/60th to 1/15th the recommended human dose on a mg/m^2 basis). Docetaxel was not mutagenic in the Ames test or the CHO/HGPRT gene mutation assays.

Docetaxel did not reduce fertility in rats when administered in multiple intravenous doses of up to 0.3 mg/kg (about 1/50th the recommended human dose on a mg/m^2 basis), but decreased testicular weights were reported. This correlates with findings of a 10-cycle toxicity study (dosing once every 21 days for 6 months) in rats and dogs in which testicular atrophy or degeneration was observed at intravenous doses of 5 mg/kg in rats and 0.375 mg/kg in dogs (about 1/3rd and 1/15th the recommended human dose on a mg/m^2 basis, respectively). An increased frequency of dosing in rats produced similar effects at lower dose levels.

14 CLINICAL STUDIES

14.1 Locally Advanced or Metastatic Breast Cancer

The efficacy and safety of Docetaxel Injection have been evaluated in locally advanced or metastatic breast cancer after failure of previous chemotherapy (alkylating agent-containing regimens or anthracycline-containing regimens).

Randomized Trials

In one randomized trial, patients with a history of prior treatment with an anthracycline-containing regimen were assigned to treatment with Docetaxel Injection (100 mg/m^2 every 3 weeks) or the combination of mitomycin (12 mg/m^2 every 6 weeks) and vinblastine (6 mg/m^2 every 3 weeks). Two hundred three patients were randomized to Docetaxel Injection and 189 to the comparator arm. Most patients had received prior chemotherapy for metastatic disease; only 27 patients on the Docetaxel Injection arm and 33 patients on the comparator arm entered the study following relapse after adjuvant therapy. Three-quarters of patients had measurable, visceral metastases. The primary endpoint was time to progression. The following table summarizes the study results (see Table 12).

Table 12 - Efficacy of Docetaxel Injection in the Treatment of Breast Cancer Patients Previously Treated with an Anthracycline-Containing Regimen (Intent-to-Treat Analysis)
Efficacy Parameter | Docetaxel | Mitomycin/ | p-value
 |  | Vinblastine
 | (n=203) | (n=189)
Median Survival | 11.4 months | 8.7 months
Risk Ratio*, Mortality
(Docetaxel: Control) | 0.73
 |  |  | p=0.01
 |  |  | Log Rank
95% CI (Risk Ratio) | 0.58 to 0.93
Median Time to Progression | 4.3 months | 2.5 months
Risk Ratio*, Progression
(Docetaxel: Control) | 0.75
 |  |  | p=0.01
 |  |  | Log Rank
95% CI (Risk Ratio) | 0.61 to 0.94
Overall Response Rate | 28.1% | 9.5% | p<0.0001
Complete Response Rate | 3.4% | 1.6% | Chi Square
*For the risk ratio, a value less than 1.00 favors docetaxel.

In a second randomized trial, patients previously treated with an alkylating-containing regimen were assigned to treatment with Docetaxel Injection (100 mg/m^2) or doxorubicin (75 mg/m^2) every 3 weeks. One hundred sixty-one patients were randomized to Docetaxel Injection and 165 patients to doxorubicin. Approximately one-half of patients had received prior chemotherapy for metastatic disease, and one-half entered the study following relapse after adjuvant therapy. Three-quarters of patients had measurable, visceral metastases. The primary endpoint was time to progression. The study results are summarized below (see Table 13).

Table 13 - Efficacy of Docetaxel Injection in the Treatment of Breast Cancer Patients Previously Treated with an Alkylating-Containing Regimen (Intent-to-Treat Analysis)
Efficacy Parameter | Docetaxel | Doxorubicin | p-value
 | (n=161) | (n=165)
Median Survival | 14.7 months | 14.3 months
Risk Ratio*, Mortality
(Docetaxel: Control) | 0.89 |  | p=0.39
 |  |  | Log Rank
95% CI (Risk Ratio) | 0.68 to 1.16
Median Time to Progression | 6.5 months | 5.3 months
Risk Ratio*, Progression
(Docetaxel: Control) | 0.93 |  | p=0.45
 |  |  | Log Rank
95% CI (Risk Ratio) | 0.71 to 1.16
Overall Response Rate | 45.3% | 29.7% | p=0.004
Complete Response Rate | 6.8% | 4.2% | Chi Square
*For the risk ratio, a value less than 1.00 favors docetaxel.

In another multicenter open-label, randomized trial (TAX313), in the treatment of patients with advanced breast cancer who progressed or relapsed after one prior chemotherapy regimen, 527 patients were randomized to receive Docetaxel Injection monotherapy 60 mg/m^2 (n=151), 75 mg/m^2 (n=188) or 100 mg/m^2 (n=188). In this trial, 94% of patients had metastatic disease and 79% had received prior anthracycline therapy. Response rate was the primary endpoint.

Response rates increased with Docetaxel Injection dose: 19.9% for the 60 mg/m^2 group compared to 22.3% for the 75 mg/m^2 and 29.8% for the 100 mg/m^2 group; pair-wise comparison between the 60 mg/m^2 and 100 mg/m^2 groups was statistically significant (p=0.037).

Single Arm Studies

Docetaxel Injection at a dose of 100 mg/m^2 was studied in six single arm studies involving a total of 309 patients with metastatic breast cancer in whom previous chemotherapy had failed. Among these, 190 patients had anthracycline-resistant breast cancer, defined as progression during an anthracycline-containing chemotherapy regimen for metastatic disease, or relapse during an anthracycline-containing adjuvant regimen. In anthracycline-resistant patients, the overall response rate was 37.9% (72/190; 95% CI: 31.0 to 44.8) and the complete response rate was 2.1%.

Docetaxel Injection was also studied in three single arm Japanese studies at a dose of 60 mg/m^2, in 174 patients who had received prior chemotherapy for locally advanced or metastatic breast cancer. Among 26 patients whose best response to an anthracycline had been progression, the response rate was 34.6% (95% CI: 17.2 to 55.7), similar to the response rate in single arm studies of 100 mg/m^2.

14.2 Adjuvant Treatment of Breast Cancer

A multicenter, open-label, randomized trial (TAX316) evaluated the efficacy and safety of Docetaxel Injection for the adjuvant treatment of patients with axillary-node-positive breast cancer and no evidence of distant metastatic disease. After stratification according to the number of positive lymph nodes (1 to 3, 4+), 1491 patients were randomized to receive either Docetaxel Injection 75 mg/m^2 administered 1-hour after doxorubicin 50 mg/m^2 and cyclophosphamide 500 mg/m^2 (TAC arm), or doxorubicin 50 mg/m^2 followed by fluorouracil 500 mg/m^2 and cyclophosphamide 500 mg/m^2 (FAC arm). Both regimens were administered every 3 weeks for 6 cycles. Docetaxel Injection was administered as a 1-hour infusion; all other drugs were given as intravenous bolus on day 1. In both arms, after the last cycle of chemotherapy, patients with positive estrogen and/or progesterone receptors received tamoxifen 20 mg daily for up to 5 years. Adjuvant radiation therapy was prescribed according to guidelines in place at participating institutions and was given to 69% of patients who received TAC and 72% of patients who received FAC.

Results from a second interim analysis (median follow-up 55 months) are as follows: In study TAX316, the docetaxel-containing combination regimen TAC showed significantly longer disease-free survival (DFS) than FAC (hazard ratio=0.74; 2-sided 95% CI=0.60, 0.92, stratified log rank p=0.0047). The primary endpoint, disease-free survival, included local and distant recurrences, contralateral breast cancer and deaths from any cause. The overall reduction in risk of relapse was 25.7% for TAC-treated patients. (see Figure 1.)

At the time of this interim analysis, based on 219 deaths, overall survival was longer for TAC than FAC (hazard ratio=0.69, 2-sided 95% CI=0.53, 0.90). (see Figure 2.) There will be further analysis at the time survival data mature.

Figure 1 - TAX316 Disease Free Survival K-M curve
Figure 2 - TAX316 Overall Survival K-M Curve

The following table describes the results of subgroup analyses for DFS and OS (see Table 14).

Table 14 - Subset Analyses-Adjuvant Breast Cancer Study
 |  | Disease Free Survival |  | Overall Survival
Patient subset | Number of | Hazard | 95% CI | Hazard | 95% CI
 | patients | ratio* |  | ratio*
No. of positive nodes
Overall | 744 | 0.74 | (0.60, 0.92) | 0.69 | (0.53, 0.90)
1 to 3 | 467 | 0.64 | (0.47, 0.87) | 0.45 | (0.29, 0.70)
4+ | 277 | 0.84 | (0.63, 1.12) | 0.93 | (0.66, 1.32)
Receptor status
Positive | 566 | 0.76 | (0.59, 0.98) | 0.69 | (0.48, 0.99)
Negative | 178 | 0.68 | (0.48, 0.97) | 0.66 | (0.44, 0.98)
*a hazard ratio of less than 1 indicates that TAC is associated with a longer disease free survival or overall survival compared to FAC.

14.3 Non-Small Cell Lung Cancer (NSCLC)

The efficacy and safety of Docetaxel Injection has been evaluated in patients with unresectable, locally advanced or metastatic non-small cell lung cancer whose disease has failed prior platinum-based chemotherapy or in patients who are chemotherapy-naive.

Monotherapy with Docetaxel Injection for NSCLC Previously Treated with Platinum-Based Chemotherapy

Two randomized, controlled trials established that a Docetaxel Injection dose of 75 mg/m^2 was tolerable and yielded a favorable outcome in patients previously treated with platinum-based chemotherapy (see below). Docetaxel Injection at a dose of 100 mg/m^2, however, was associated with unacceptable hematologic toxicity, infections, and treatment-related mortality and this dose should not be used [see Boxed Warning, Dosage and Administration (2.7), Warnings and Precautions (5.3)].

One trial (TAX317), randomized patients with locally advanced or metastatic non-small cell lung cancer, a history of prior platinum-based chemotherapy, no history of taxane exposure, and an ECOG performance status ≤2 to Docetaxel Injection or best supportive care. The primary endpoint of the study was survival. Patients were initially randomized to Docetaxel Injection 100 mg/m^2 or best supportive care, but early toxic deaths at this dose led to a dose reduction to Docetaxel Injection 75 mg/m^2. A total of 104 patients were randomized in this amended study to either Docetaxel Injection 75 mg/m^2 or best supportive care.

In a second randomized trial (TAX320), 373 patients with locally advanced or metastatic non-small cell lung cancer, a history of prior platinum-based chemotherapy, and an ECOG performance status ≤2 were randomized to Docetaxel Injection 75 mg/m^2, Docetaxel Injection 100 mg/m^2 and a treatment in which the investigator chose either vinorelbine 30 mg/m^2 days 1, 8, and 15 repeated every 3 weeks or ifosfamide 2 g/m^2 days 1 to 3 repeated every 3 weeks. Forty percent of the patients in this study had a history of prior paclitaxel exposure. The primary endpoint was survival in both trials. The efficacy data for the Docetaxel Injection 75 mg/m^2 arm and the comparator arms are summarized in Table 15 and Figures 3 and 4 showing the survival curves for the two studies.

Table 15 - Efficacy of Docetaxel Injection in the Treatment of Non-Small Cell Lung Cancer Patients Previously Treated with a Platinum-Based Chemotherapy Regimen (Intent-to-Treat Analysis)
 | TAX317 |  | TAX320
 | Docetaxel | Best | Docetaxel | Control
 | 75 mg/m^2 | Supportive Care | 75 mg/m^2 | (V/I*)
 | n=55 | n=49 | n=125 | n=123
Overall Survival
Log-rank Test | p=0.01 |  | p=0.13
Risk Ratio††, Mortality
(Docetaxel: Control) | 0.56 |  | 0.82
95% CI (Risk Ratio) | (0.35, 0.88) |  | (0.63, 1.06)
Median Survival | 7.5 months** | 4.6 months | 5.7 months | 5.6 months
95% CI | (5.5, 12.8) | (3.7, 6.1) | (5.1, 7.1) | (4.4, 7.9)
% 1-year Survival | 37%**† | 12% | 30%**† | 20%
95% CI | (24, 50) | (2, 23) | (22, 39) | (13, 27)
Time to Progression | 12.3 weeks** | 7.0 weeks | 8.3 weeks | 7.6 weeks
95% CI | (9.0, 18.3) | (6.0, 9.3) | (7.0, 11.7) | (6.7, 10.1)
Response Rate | 5.5% |  | 5.7% | 0.8%
 |  | Not
95% CI | (1.1, 15.1) | Applicable | (2.3, 11.3) | (0.0, 4.5)
* Vinorelbine/Ifosfamide
** p≤0.05
† uncorrected for multiple comparisons
†† a value less than 1.00 favors docetaxel

Only one of the two trials (TAX317) showed a clear effect on survival, the primary endpoint; that trial also showed an increased rate of survival to one year. In the second study (TAX320) the rate of survival at one year favored Docetaxel Injection 75 mg/m^2.

Figure 3 - TAX317 Survival K-M Curves - Docetaxel Injection 75 mg/m^2 vs. Best Supportive Care

Figure 4 - TAX320 Survival K-M Curves - Docetaxel Injection 75 mg/m^2 vs. Vinorelbine or Ifosfamide Control

Patients treated with Docetaxel Injection at a dose of 75 mg/m^2 experienced no deterioration in performance status and body weight relative to the comparator arms used in these trials.

Combination Therapy with Docetaxel Injection for Chemotherapy-Naive NSCLC

In a randomized controlled trial (TAX326), 1218 patients with unresectable stage IIIB or IV NSCLC and no prior chemotherapy were randomized to receive one of three treatments: Docetaxel Injection 75 mg/m^2 as a 1 hour infusion immediately followed by cisplatin 75 mg/m^2 over 30 to 60 minutes every 3 weeks; vinorelbine 25 mg/m^2 administered over 6 to 10 minutes on days 1, 8, 15, 22 followed by cisplatin 100 mg/m^2 administered on day 1 of cycles repeated every 4 weeks; or a combination of Docetaxel Injection and carboplatin.

The primary efficacy endpoint was overall survival. Treatment with Docetaxel Injection+cisplatin did not result in a statistically significantly superior survival compared to vinorelbine+cisplatin (see table below). The 95% confidence interval of the hazard ratio (adjusted for interim analysis and multiple comparisons) shows that the addition of Docetaxel Injection to cisplatin results in an outcome ranging from a 6% inferior to a 26% superior survival compared to the addition of vinorelbine to cisplatin. The results of a further statistical analysis showed that at least (the lower bound of the 95% confidence interval) 62% of the known survival effect of vinorelbine when added to cisplatin (about a 2-month increase in median survival; Wozniak et al. JCO, 1998) was maintained. The efficacy data for the Docetaxel Injection+cisplatin arm and the comparator arm are summarized in Table 16.

Table 16 - Survival Analysis of Docetaxel Injection in Combination Therapy for Chemotherapy-Naive NSCLC
Comparison | Docetaxel Injection+Cisplatin | Vinorelbine+Cisplatin
 | n=408 | n=405
Kaplan-Meier Estimate of Median Survival | 10.9 months | 10.0 months
p-valuea | 0.122
Estimated Hazard Ratiob | 0.88
Adjusted 95% CIc | (0.74, 1.06)
a From the superiority test (stratified log rank) comparing Docetaxel Injection+cisplatin to vinorelbine+cisplatin
bHazard ratio of Docetaxel Injection+cisplatin vs. vinorelbine+cisplatin. A hazard ratio of less than 1 indicates that Docetaxel Injection+cisplatin is associated with a longer survival.
cAdjusted for interim analysis and multiple comparisons.

The second comparison in the same three-arm study, vinorelbine+cisplatin versus Docetaxel Injection+carboplatin, did not demonstrate superior survival associated with the Docetaxel Injection arm (Kaplan-Meier estimate of median survival was 9.1 months for Docetaxel Injection+carboplatin compared to 10.0 months on the vinorelbine+cisplatin arm) and the Docetaxel Injection+carboplatin arm did not demonstrate preservation of at least 50% of the survival effect of vinorelbine added to cisplatin. Secondary endpoints evaluated in the trial included objective response and time to progression. There was no statistically significant difference between Docetaxel Injection+cisplatin and vinorelbine+cisplatin with respect to objective response and time to progression (see Table 17).

Table 17 - Response and TTP Analysis of Docetaxel Injection in Combination Therapy for Chemotherapy-Naive NSCLC
Endpoint | Docetaxel Injection+Cisplatin | Vinorelbine+Cisplatin | p-value
Objective Response Rate | 31.6% | 24.4% | Not Significant
(95% CI)a | (26.5%, 36.8%) | (19.8%, 29.2%)
Median Time to
Progressionb | 21.4 weeks | 22.1 weeks | Not Significant
(95% CI)a | (19.3, 24.6) | (18.1, 25.6)
aAdjusted for multiple comparisons.
bKaplan-Meier estimates.

14.4 Castration-Resistant Prostate Cancer

The safety and efficacy of Docetaxel Injection in combination with prednisone in patients with metastatic castration-resistant prostate cancer were evaluated in a randomized multicenter active control trial. A total of 1006 patients with Karnofsky Performance Status (KPS) ≥60 were randomized to the following treatment groups:

- Docetaxel Injection 75 mg/m^2 every 3 weeks for 10 cycles.
- Docetaxel Injection 30 mg/m^2 administered weekly for the first 5 weeks in a 6-week cycle for 5 cycles.
- Mitoxantrone 12 mg/m^2 every 3 weeks for 10 cycles.

All 3 regimens were administered in combination with prednisone 5 mg twice daily, continuously.

In the Docetaxel Injection every three week arm, a statistically significant overall survival advantage was demonstrated compared to mitoxantrone. In the Docetaxel Injection weekly arm, no overall survival advantage was demonstrated compared to the mitoxantrone control arm. Efficacy results for the Docetaxel Injection every 3 week arm versus the control arm are summarized in Table 18 and Figure 5.

Table 18 - Efficacy of Docetaxel Injection in the Treatment of Patients with Metastatic Castration-Resistant Prostate Cancer (Intent-to-Treat Analysis)
 | Docetaxel Injection+Prednisone | Mitoxantrone+Prednisone
 | every 3 weeks | every 3 weeks
Number of patients | 335 | 337
Median survival (months) | 18.9 | 16.5
95% CI | (17.0 to 21.2) | (14.4 to 18.6)
Hazard ratio | 0.761 | --
95% CI | (0.619 to 0.936) | --
p-value* | 0.0094 | --
*Stratified log rank test. Threshold for statistical significance = 0.0175 because of 3 arms.

Figure 5 - TAX327 Survival K-M Curves

14.5 Gastric Adenocarcinoma

A multicenter, open-label, randomized trial was conducted to evaluate the safety and efficacy of Docetaxel Injection for the treatment of patients with advanced gastric adenocarcinoma, including adenocarcinoma of the gastroesophageal junction, who had not received prior chemotherapy for advanced disease. A total of 445 patients with KPS >70 were treated with either Docetaxel Injection (T) (75 mg/m^2 on day 1) in combination with cisplatin (C) (75 mg/m^2 on day 1) and fluorouracil (F) (750 mg/m^2 per day for 5 days) or cisplatin (100 mg/m^2 on day 1) and fluorouracil (1000 mg/m^2 per day for 5 days). The length of a treatment cycle was 3 weeks for the TCF arm and 4 weeks for the CF arm. The demographic characteristics were balanced between the two treatment arms. The median age was 55 years, 71% were male, 71% were Caucasian, 24% were 65 years of age or older, 19% had a prior curative surgery and 12% had palliative surgery. The median number of cycles administered per patient was 6 (with a range of 1 to 16) for the TCF arm compared to 4 (with a range of 1 to 12) for the CF arm. Time to progression (TTP) was the primary endpoint and was defined as time from randomization to disease progression or death from any cause within 12 weeks of the last evaluable tumor assessment or within 12 weeks of the first infusion of study drugs for patients with no evaluable tumor assessment after randomization. The hazard ratio (HR) for TTP was 1.47 (CF/TCF, 95% CI: 1.19 to 1.83) with a significantly longer TTP (p=0.0004) in the TCF arm. Approximately 75% of patients had died at the time of this analysis. Overall survival was significantly longer (p=0.0201) in the TCF arm with a HR of 1.29 (95% CI: 1.04 to 1.61). Efficacy results are summarized in Table 19 and Figures 6 and 7.

Table 19 - Efficacy of Docetaxel Injection in the Treatment of Patients with Gastric Adenocarcinoma
Endpoint | TCF | CF
 | n=221 | n=224
Median TTP (months) | 5.6 | 3.7
(95% CI) | (4.86 to 5.91) | (3.45 to 4.47)
Hazard ratio† | 0.68
(95% CI) | (0.55 to 0.84)
*p-value | 0.0004
Median survival (months) | 9.2 | 8.6
(95% CI) | (8.38 to 10.58) | (7.16 to 9.46)
Hazard ratio† | 0.77
(95% CI) | (0.62 to 0.96)
*p-value | 0.0201
Overall Response Rate (CR+PR) (%) | 36.7 | 25.4
p-value | 0.0106
*Unstratified log-rank test
†For the hazard ratio (TCF/CF), values less than 1.00 favor the Docetaxel Injection arm.

Subgroup analyses were consistent with the overall results across age, gender and race.

Figure 6 - Gastric Cancer Study (TAX325) Time to Progression K-M Curve
Figure 7 - Gastric Cancer Study (TAX325) Survival K-M Curve

14.6 Head and Neck Cancer

Induction chemotherapy followed by radiotherapy (TAX323)

The safety and efficacy of Docetaxel Injection in the induction treatment of patients with squamous cell carcinoma of the head and neck (SCCHN) was evaluated in a multicenter, open-label, randomized trial (TAX323). In this study, 358 patients with inoperable locally advanced SCCHN, and WHO performance status 0 or 1, were randomized to one of two treatment arms. Patients on the Docetaxel Injection arm received Docetaxel Injection (T) 75 mg/m^2 followed by cisplatin (P) 75 mg/m^2 on Day 1, followed by fluorouracil (F) 750 mg/m^2 per day as a continuous infusion on Days 1 to 5. The cycles were repeated every three weeks for 4 cycles. Patients whose disease did not progress received radiotherapy (RT) according to institutional guidelines (TPF/RT). Patients on the comparator arm received cisplatin (P) 100 mg/m^2 on Day 1, followed by fluorouracil (F) 1000 mg/m^2/day as a continuous infusion on Days 1 to 5. The cycles were repeated every three weeks for 4 cycles. Patients whose disease did not progress received RT according to institutional guidelines (PF/RT). At the end of chemotherapy, with a minimal interval of 4 weeks and a maximal interval of 7 weeks, patients whose disease did not progress received radiotherapy (RT) according to institutional guidelines. Locoregional therapy with radiation was delivered either with a conventional fraction regimen (1.8 Gy to 2.0 Gy once a day, 5 days per week for a total dose of 66 to 70 Gy) or with an accelerated/hyperfractionated regimen (twice a day, with a minimum interfraction interval of 6 hours, 5 days per week, for a total dose of 70 to 74 Gy, respectively). Surgical resection was allowed following chemotherapy, before or after radiotherapy.

The primary endpoint in this study, progression-free survival (PFS), was significantly longer in the TPF arm compared to the PF arm, p=0.0077 (median PFS: 11.4 vs. 8.3 months, respectively) with an overall median follow-up time of 33.7 months. Median overall survival with a median follow-up of 51.2 months was also significantly longer in favor of the TPF arm compared to the PF arm (median OS: 18.6 vs. 14.2 months, respectively). Efficacy results are presented in Table 20 and Figures 8 and 9.

Table 20 - Efficacy of Docetaxel Injection in the Induction Treatment of Patients with Inoperable Locally Advanced SCCHN (Intent-to-Treat Analysis)
Endpoint | Docetaxel Injection+
 | Cisplatin+ | Cisplatin+
 | Fluorouracil | Fluorouracil
 | n=177 | n=181
Median progression free survival (months) | 11.4 | 8.3
(95% CI) | (10.1 to 14.0) | (7.4 to 9.1)
Adjusted Hazard ratio | 0.71
(95% CI) | (0.56 to 0.91)
*p-value | 0.0077
Median survival (months) | 18.6 | 14.2
(95% CI) | (15.7 to 24.0) | (11.5 to 18.7)
Hazard ratio | 0.71
(95% CI) | (0.56 to 0.90)
**p-value | 0.0055
Best overall response (CR + PR) to
chemotherapy (%) | 67.8 | 53.6
(95% CI) | (60.4 to 74.6) | (46.0 to 61.0)
***p-value | 0.006
Best overall response (CR + PR) to study
treatment [chemotherapy +/- radiotherapy] (%) | 72.3 | 58.6
(95% CI) | (65.1 to 78.8) | (51.0 to 65.8)
***p-value | 0.006
A Hazard ratio of less than 1 favors Docetaxel Injection+Cisplatin+Fluorouracil
* Stratified log-rank test based on primary tumor site
** Stratified log-rank test, not adjusted for multiple comparisons
*** Chi square test, not adjusted for multiple comparisons

Figure 8 - TAX323 Progression-Free Survival K-M Curve
Figure 9 - TAX323 Overall Survival K-M Curve

Induction chemotherapy followed by chemoradiotherapy (TAX324)

The safety and efficacy of Docetaxel Injection in the induction treatment of patients with locally advanced (unresectable, low surgical cure, or organ preservation) SCCHN was evaluated in a randomized, multicenter open-label trial (TAX324). In this study, 501 patients, with locally advanced SCCHN, and a WHO performance status of 0 or 1, were randomized to one of two treatment arms. Patients on the Docetaxel Injection arm received Docetaxel Injection (T) 75 mg/m^2 by intravenous infusion on day 1 followed by cisplatin (P) 100 mg/m^2 administered as a 30-minute to three-hour intravenous infusion, followed by the continuous intravenous infusion of fluorouracil (F) 1000 mg/m^2/day from day 1 to day 4. The cycles were repeated every 3 weeks for 3 cycles. Patients on the comparator arm received cisplatin (P) 100 mg/m^2 as a 30-minute to three-hour intravenous infusion on day 1 followed by the continuous intravenous infusion of fluorouracil (F) 1000 mg/m^2/day from day 1 to day 5. The cycles were repeated every 3 weeks for 3 cycles.

All patients in both treatment arms who did not have progressive disease were to receive 7 weeks of chemoradiotherapy (CRT) following induction chemotherapy 3 to 8 weeks after the start of the last cycle. During radiotherapy, carboplatin (AUC 1.5) was given weekly as a one-hour intravenous infusion for a maximum of 7 doses. Radiation was delivered with megavoltage equipment using once daily fractionation (2 Gy per day, 5 days per week for 7 weeks for a total dose of 70 to 72 Gy). Surgery on the primary site of disease and/or neck could be considered at anytime following completion of CRT.

The primary efficacy endpoint, overall survival (OS), was significantly longer (log-rank test, p=0.0058) with the Docetaxel Injection-containing regimen compared to PF [median OS: 70.6 versus 30.1 months respectively, hazard ratio (HR)=0.70, 95% confidence interval (CI)= 0.54 – 0.90]. Overall survival results are presented in Table 21 and Figure 10.

Table 21 - Efficacy of Docetaxel Injection in the Induction Treatment of Patients with Locally Advanced SCCHN (Intent-to-Treat Analysis)
 | Docetaxel Injection+ | Cisplatin+
 | Cisplatin+Fluorouracil | Fluorouracil
Endpoint | n=255 | n=246
Median overall survival (months) | 70.6 | 30.1
(95% CI) | (49.0 to NE) | (20.9 to 51.5)
Hazard ratio: | 0.70
(95% CI) | (0.54 to 0.90)
*p-value | 0.0058
A Hazard ratio of less than 1 favors Docetaxel Injection+cisplatin+fluorouracil
* unadjusted log-rank test
NE - not estimable

Figure 10 - TAX324 Overall Survival K-M Curve

15 REFERENCES

1. “OSHA Hazardous Drugs.” http://www.osha.gov/SLTC/hazardousdrugs/index.html

16 HOW SUPPLIED/STORAGE AND HANDLING

16.1 How Supplied

Docetaxel Injection, USP is supplied as a sterile, pyrogen-free, non-aqueous solution in single-dose, flip-top glass vials, as a clear, viscous, colorless to pale yellow solution, without macroscopic particles in solution at 20 mg/mL concentration, in the following package strengths:

Docetaxel Injection USP, 20 mg/mL available as one vial per carton NDC 45963-734-54

Docetaxel Injection USP, 80 mg/4 mL (20 mg/mL) available as one vial per carton NDC 45963-765-52

Discard unused portion. The vial stopper is not made with natural rubber latex.

16.2 Storage

Store at 25°C (77°F); excursions permitted to 15° to 30°C (59° to 86°F). Retain in the original package to protect from light.

16.3 Handling and Disposal

Docetaxel Injection is a hazardous drug. Follow applicable special handling and disposal procedures.

17 PATIENT COUNSELING INFORMATION

Advise the patient to read the FDA-approved Patient Labeling (Patient Information).

Bone Marrow Suppression

Advise patients that periodic assessment of their blood count will be performed to detect neutropenia, thrombocytopenia, and/ or anemia [see Contraindications (4), Warnings and Precautions (5.3)]. Instruct patients to monitor their temperature frequently and immediately report any occurrence of fever.

Enterocolitis and Neutropenic Colitis

Advise patients of the symptoms of colitis, such as abdominal pain or tenderness, and/or diarrhea, with or without fever, and instruct patients to promptly contact their healthcare provider if they experience these symptoms [see Dosage and Administration (2.7) and Warnings and Precautions (5.4)].

Hypersensitivity Reactions

Ask patients whether they have previously received paclitaxel therapy, and if they have experienced a hypersensitivity reaction to paclitaxel. Instruct patients to immediately report to their healthcare provider signs of a hypersensitivity reaction [see Contraindications (4), Warnings and Precautions (5.5)].

Fluid Retention

Advise patients to report signs of fluid retention such as peripheral edema in the lower extremities, weight gain, and dyspnea immediately to their healthcare provider [see Warnings and Precautions (5.6)].

Second Primary Malignancies

Advise patients on the risk of second primary malignancies during treatment with Docetaxel Injection [see Warnings and Precautions (5.7)].

Cutaneous Reactions

Advise patients that localized erythema of the extremities and severe skin toxicities may occur. Instruct patients to immediately report severe cutaneous reactions to their healthcare provider [see Dosage and Administration (2.7) and Warnings and Precautions (5.8)].

Neurologic Reactions

Advise patients that neurosensory symptoms or peripheral neuropathy may occur. Instruct patients to immediately report neurologic reactions to their healthcare provider [see Dosage and Administration (2.7) and Warnings and Precautions (5.9)].

Eye Disorders

Advise patients that vision disturbances and excessive tearing are associated with Docetaxel Injection administration. Instruct patients to immediately report any vision changes to their healthcare provider [see Warnings and Precautions (5.10)].

Gastrointestinal Reactions

Explain to patients that nausea, vomiting, diarrhea, and constipation are associated with Docetaxel Injection administration. Instruct patients to report any severe events to their healthcare provider [see Adverse Reactions (6)].

Cardiac Disorders

Advise patients to report any irregular and/or rapid heartbeat, severe shortness of breath, dizziness, and/or fainting immediately to their healthcare provider [see Adverse Reactions (6)].

Other Common Adverse Reactions

Advise patients that other common adverse reactions associated with Docetaxel Injection may include alopecia (cases of permanent hair loss have been reported), asthenia, anorexia, dysgeusia, mucositis, myalgia, nail disorders, or pain. Instruct patients to report these reactions to their healthcare provider if serious events occur [see Adverse Reactions (6)].

Importance of Corticosteroids

Explain the significance of oral corticosteroids such as dexamethasone administration to the patient to help facilitate compliance. Instruct patients to report to their healthcare provider if they were not compliant with the oral corticosteroid regimen [see Dosage and Administration (2.6)].

Embryo-Fetal Toxicity

Docetaxel Injection can cause fetal harm. Advise patients to inform their healthcare provider of a known or suspected pregnancy. Advise patients to avoid becoming pregnant while receiving this drug. Advise female patients of reproductive potential to use effective contraceptives during treatment and for 2 months after the last dose of Docetaxel Injection. Advise male patients with female partners of reproductive potential to use effective contraception during treatment and for 4 months after the last dose of Docetaxel Injection [see Warnings and Precautions (5.12), and Use in Specific Populations (8.1, 8.3)].

Lactation

Advise women not to breastfeed during Docetaxel Injection treatment and for 1 week after the last dose [see Use in Specific Populations (8.2)].

Infertility

Advise males of reproductive potential that Docetaxel Injection may impair fertility [see Nonclinical Toxicology (13.1)].

Alcohol Content in Docetaxel Injection

Explain to patients the possible effects of the alcohol content in Docetaxel Injection, including possible effects on the central nervous system [see Warnings and Precautions (5.13)].

Tumor Lysis Syndrome

Advise patients of the potential risk of tumor lysis syndrome and to immediately report any signs or symptoms associated with this event (nausea, vomiting, confusion, shortness of breath, seizure, irregular heartbeat, dark or cloudy urine, reduced amount of urine, unusual tiredness, muscle cramps) to their healthcare provider. Advise patients of the importance of keeping scheduled appointment for blood work or other laboratory tests and of drinking adequate fluids to avoid dehydration. [see Warnings and Precautions (5.14)].

Ability to Drive or Operate Machines

Explain to patients that Docetaxel Injection may impair their ability to drive or operate machines due to its side effects [see Adverse Reactions (6)] or due to the alcohol content of Docetaxel Injection [see Warnings and Precautions (5.13)]. Advise them not to drive or use machines if they experience these side effects during treatment.

Drug Interactions

Inform patients about the risk of drug interactions and the importance of providing a list of prescription and non-prescription drugs to their healthcare provider [see Drug Interactions (7)].

Manufactured In Romania By:
Sindan Pharma SRL
Bucharest 1, Romania 011171

Manufactured For:
Teva Pharmaceuticals
Parsippany, NJ 07054

Rev. J 8/2024

PATIENT INFORMATION
Docetaxel (doe-se-tax-el) Injection
for intravenous use

What is the most important information I should know about Docetaxel Injection?

Docetaxel Injection can cause serious side effects, including death.

- The chance of death in people who receive Docetaxel Injection is higher if you:
  - have liver problems
  - receive high doses of Docetaxel Injection
  - have non-small cell lung cancer and have been treated with chemotherapy medicines that contain platinum
- Docetaxel Injection can affect your blood cells. Your healthcare provider should do routine blood tests during treatment with Docetaxel Injection. This will include regular checks of your white blood cell counts. If your white blood cells are too low, your healthcare provider may not treat you with Docetaxel Injection until you have enough white blood cells. People with low white blood cell counts can develop life-threatening infections. The earliest sign of infection may be fever. Follow your healthcare provider’s instructions for how often to take your temperature during treatment with Docetaxel Injection. Call your healthcare provider right away if you have a fever.
- Swelling (inflammation) of the small intestine and colon. This can happen at any time during treatment and could lead to death as early as the first day you get symptoms. Tell your healthcare provider right away if you develop new or worse symptoms of intestinal problems, including stomach (abdominal) pain or tenderness or diarrhea, with or without fever.
- Severe allergic reactions are medical emergencies that can happen in people who receive Docetaxel Injection and can lead to death. You may be at higher risk of developing a severe allergic reaction to Docetaxel Injection if you are allergic to paclitaxel. Your healthcare provider will monitor you closely for allergic reactions during your Docetaxel Injection infusion.

Tell your healthcare provider right away if you have any of these signs of a severe allergic reaction:

- trouble breathing
- sudden swelling of your face, lips, tongue, throat, or trouble swallowing
- hives (raised bumps), rash, or redness all over your body

- Your body may hold too much fluid (severe fluid retention) during treatment with Docetaxel Injection. This can be life threatening. To decrease the chance of this happening, you must take another medicine, a corticosteroid, before each Docetaxel Injection treatment. You must take the corticosteroid exactly as your healthcare provider tells you. Tell your healthcare provider or nurse before your Docetaxel Injection treatment if you forgot to take your corticosteroid dose or do not take it as your healthcare provider tells you. Tell your healthcare provider right away if you have swelling in your legs or feet, weight gain or shortness of breath.
- Risk of new cancers. An increase in new (second) cancers has happened in people treated with Docetaxel Injection together with certain other anticancer treatments. This includes certain blood cancers, such as acute myeloid leukemia (AML), myelodysplastic syndrome (MDS), non-Hodgkin’s Lymphoma (NHL), and kidney cancer.
  - Changes in blood counts due to leukemia and other blood disorders may occur years after treatment with Docetaxel Injection.
    Your healthcare provider will check you for new cancers during and after your treatment with Docetaxel Injection.
- Severe skin problems.
  Tell your healthcare provider right away if you have any of these signs of a severe skin reaction:
  - redness and swelling of your arms and legs.
  - blistering, peeling, or bleeding on any part of your skin (including your lips, eyes, mouth, nose, genitals, hands or feet) with or without a rash. You may also have flu-like symptoms such as fever, chills, or muscle aches.
  - red, scaly rash all over your body with blisters, small red or white bumps under the skin that contain pus (pustules), and fever.

What is Docetaxel Injection?

Docetaxel Injection is a prescription anticancer medicine used to treat certain people with:

- breast cancer
- non-small cell lung cancer
- prostate cancer
- stomach cancer
- head and neck cancer

It is not known if Docetaxel Injection is effective in children.

Do not receive Docetaxel Injection if you:

- have a low white blood cell count.
- have had a severe allergic reaction to:
  - docetaxel, the active ingredient in Docetaxel Injection, or

- any other medicines that contain polysorbate 80. Ask your healthcare provider or pharmacist if you are not sure.

See “What is the most important information I should know about Docetaxel Injection?” for the signs and symptoms of a severe allergic reaction.

See the end of this Patient Information for a complete list of the ingredients in Docetaxel Injection.

Before you receive Docetaxel Injection, tell your healthcare provider about all of your medical conditions, including if you:

- are allergic to any medicines, including paclitaxel. See “Do not receive Docetaxel Injection if you”.
- have liver problems
- have kidney problems
- are pregnant or plan to become pregnant. Docetaxel Injection can harm your unborn baby. You should not become pregnant during treatment with Docetaxel Injection. Tell your healthcare provider if you become pregnant or you think you may be pregnant during treatment with Docetaxel Injection.
  Females who are able to become pregnant:

- Your healthcare provider will check to see if you are pregnant before you start treatment with Docetaxel Injection.
- You should use effective birth control (contraception) during treatment with Docetaxel Injection and for 2 months after the last dose.
  Males with female partners who are able to become pregnant should use effective birth control during treatment with Docetaxel Injection and for 4 months after the last dose.
  Talk to your healthcare provider if you have questions about birth control options that are right for you.

- are breastfeeding or plan to breastfeed. It is not known if Docetaxel Injection passes into your breast milk. Do not breastfeed during treatment with Docetaxel Injection and for 1 week after the last dose.

Tell your healthcare provider about all the medicines you take, including prescription and over-the-counter medicines, vitamins, and herbal supplements. Docetaxel Injection may affect the way other medicines work, and other medicines may affect the way Docetaxel Injection works.

Know the medicines you take. Keep a list of them to show your healthcare provider and pharmacist when you get a new medicine.

How will I receive Docetaxel Injection?

- Docetaxel Injection will be given to you as an intravenous (IV) injection into your vein, usually over 1 hour.
- Docetaxel Injection is usually given every 3 weeks.
- Your healthcare provider will decide how long you will receive treatment with Docetaxel Injection.
- Your healthcare provider will check your blood cell counts and other blood tests during your treatment with Docetaxel Injection to check for side effects of Docetaxel Injection.
- Your healthcare provider may stop your treatment, change the timing of your treatment, or change the dose of your treatment if you have certain side effects while receiving Docetaxel Injection.

What are the possible side effects of Docetaxel Injection?

Docetaxel Injection may cause serious side effects including death.

- See “What is the most important information I should know about Docetaxel Injection?”
- Neurologic problems. Neurologic symptoms are common in people who receive Docetaxel Injection but can be severe. Tell your healthcare provider right away if you have numbness, tingling, or burning in your hands or feet (peripheral neuropathy) or weakness of your legs, feet, arms, or hands (motor weakness).
- Vision problems including blurred vision or loss of vision. Tell your healthcare provider right away if you have any vision changes.
- Docetaxel Injection contains alcohol. The alcohol content in Docetaxel Injection may impair your ability to drive or use machinery right after receiving Docetaxel Injection. Consider whether you should drive, operate machinery or do other dangerous activities right after you receive Docetaxel Injection treatment.
- Tumor lysis syndrome (TLS). TLS is caused by the fast breakdown of cancer cells. TLS can cause kidney failure, the need for dialysis treatment, or heart problems, and may lead to death. Your healthcare provider will do blood tests to check for TLS when you first start treatment and during treatment with Docetaxel Injection. Tell your healthcare provider right away if you have any symptoms of TLS during treatment with Docetaxel Injection, including:

- nausea
- vomiting
- confusion
- shortness of breath

- irregular heartbeat
- dark or cloudy urine
- reduced amount of urine
- unusual tiredness
- muscle cramps

- You may experience side effects of Docetaxel Injection that may impair your ability to drive, use tools, or operate machines. If this happens, do not drive or use any tools or machines before discussing with your healthcare provider.

The most common side effects of Docetaxel Injection include:

- infections
- low white blood cells (help fight infections), low red blood cells (anemia) and low platelets (help blood to clot)
- allergic reactions (See “What is the most important information I should know about Docetaxel Injection?”)
- changes in your sense of taste
- shortness of breath
- constipation
- decreased appetite
- changes in your fingernails or toenails
- swelling of your hands, face or feet

- feeling weak or tired
- joint and muscle pain
- nausea and vomiting
- diarrhea
- mouth or lip sores
- hair loss: in some people, permanent hair loss has been reported
- redness of the eye, excess tearing
- skin reactions at the site of Docetaxel Injection administration such as increased skin pigmentation, redness, tenderness, swelling, warmth or dryness of the skin
- tissue damage if Docetaxel Injection leaks out of the vein into the tissues

Tell your healthcare provider if you have a fast or irregular heartbeat, severe shortness of breath, dizziness or fainting during your infusion. If any of these events occurs after your infusion, get medical help right away.

Docetaxel Injection may affect fertility in males. Talk to your healthcare provider if this is a concern for you.

These are not all of the possible side effects of Docetaxel Injection. For more information, ask your healthcare provider or pharmacist.

Call your healthcare provider for medical advice about side effects. You may report side effects to FDA at 1-800-FDA-1088.

General information about the safe and effective use of Docetaxel Injection.
Medicines are sometimes prescribed for purposes other than those listed in this Patient Information. You can ask your pharmacist or healthcare provider for information about Docetaxel Injection that is written for health professionals.

What are the ingredients in Docetaxel Injection?
Active ingredient: docetaxel
Inactive ingredients: citric acid anhydrous, kollidon 12 PF (povidone P12), polysorbate 80 and ethanol.

Manufactured In Romania By: Sindan Pharma SRL, Bucharest 1, Romania 011171
Manufactured For: Teva Pharmaceuticals, Parsippany, NJ 07054
For more information call 1-888-838-2872.

This Patient Information has been approved by the U.S. Food and Drug Administration. Revised: J 8/2024

PACKAGE LABEL.PRINCIPAL DISPLAY PANEL

NDC 45963-734-54

Docetaxel Injection, USP
20 mg/mL

For Intravenous Infusion Only
READY TO ADD TO
INFUSION SOLUTION

Warning: Hazardous Drug

Rx only

Contains 1 mL Single-Dose Vial
Discard Unused Portion.

PACKAGE LABEL.PRINCIPAL DISPLAY PANEL

NDC 45963-765-52

Docetaxel Injection, USP
80 mg/4 mL
(20 mg/mL)

For Intravenous Infusion Only
READY TO ADD TO
INFUSION SOLUTION

Warning: Hazardous Drug

Rx only

Contains 4 mL Single-Dose Vial
Discard Unused Portion.